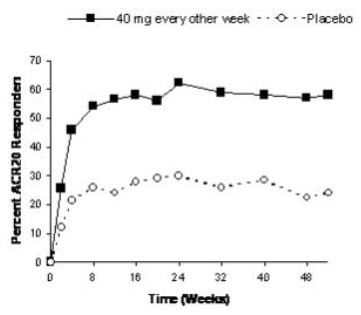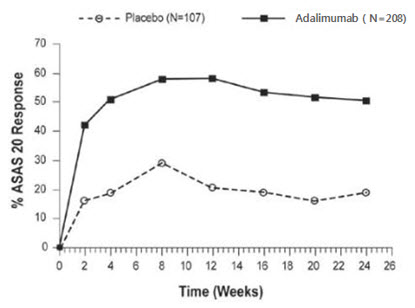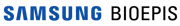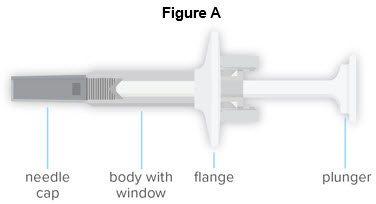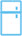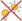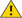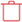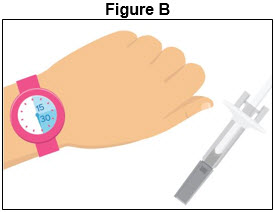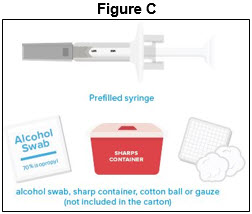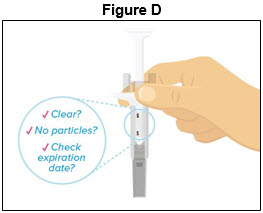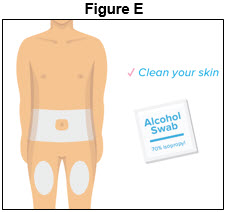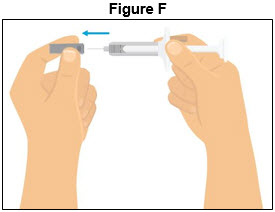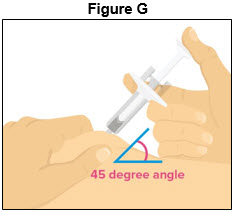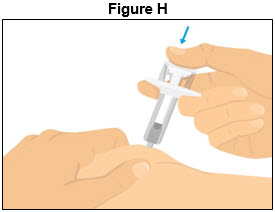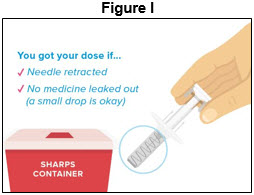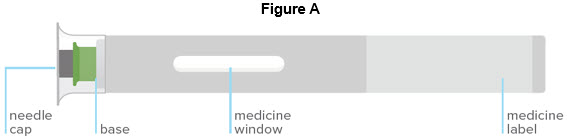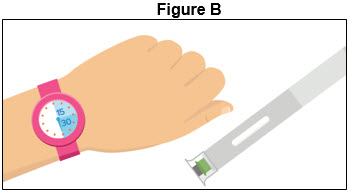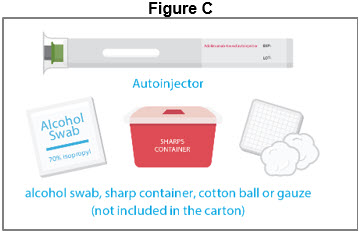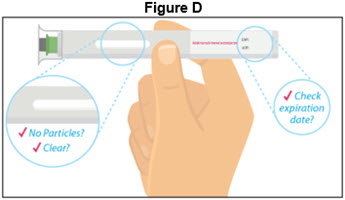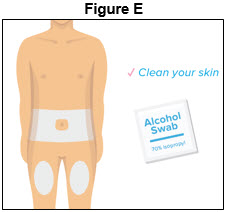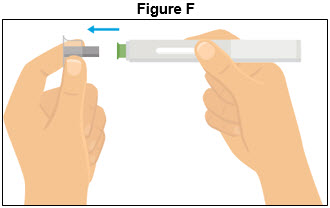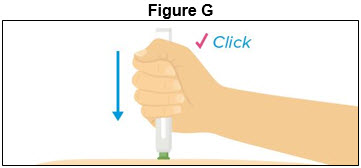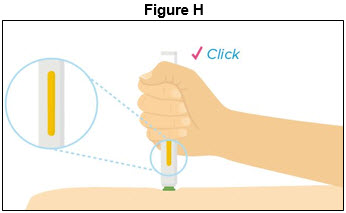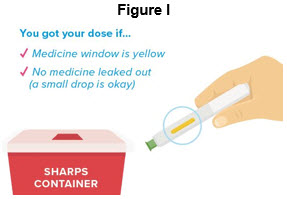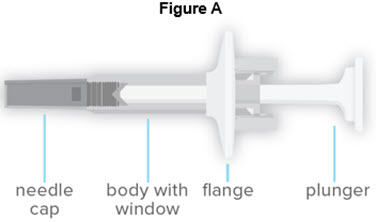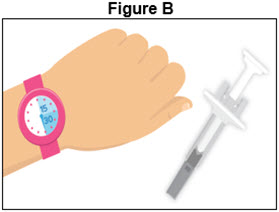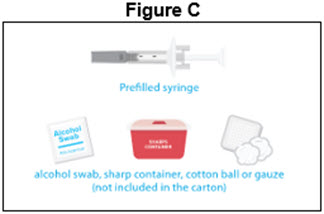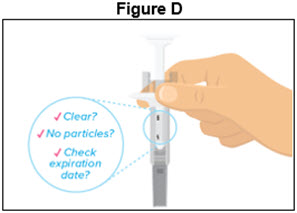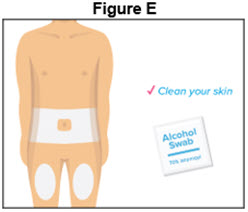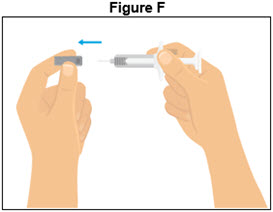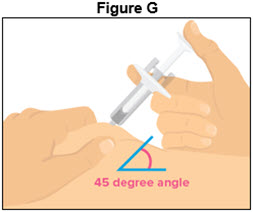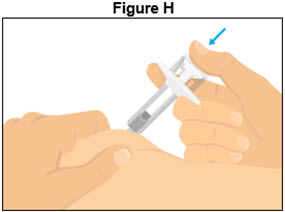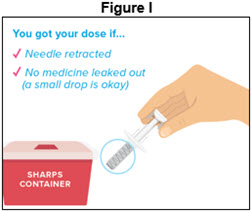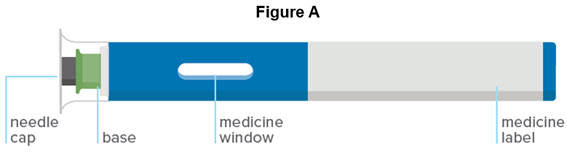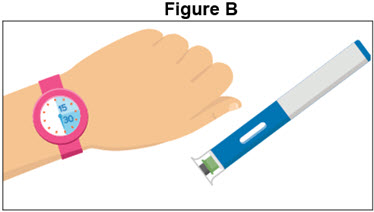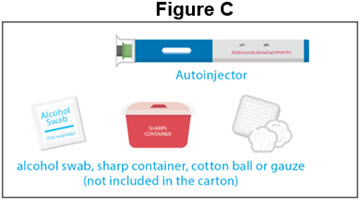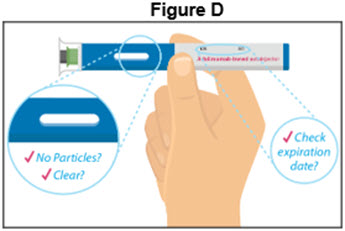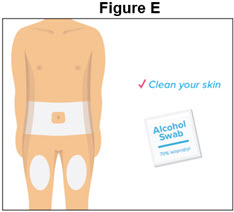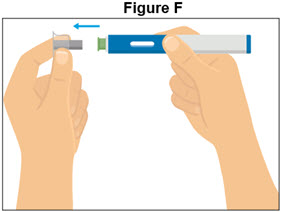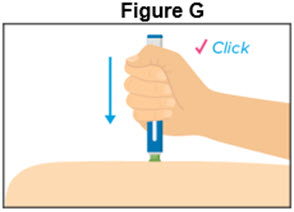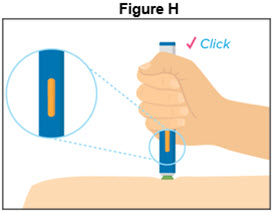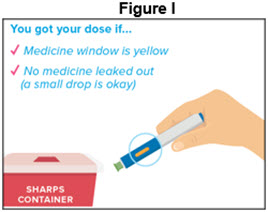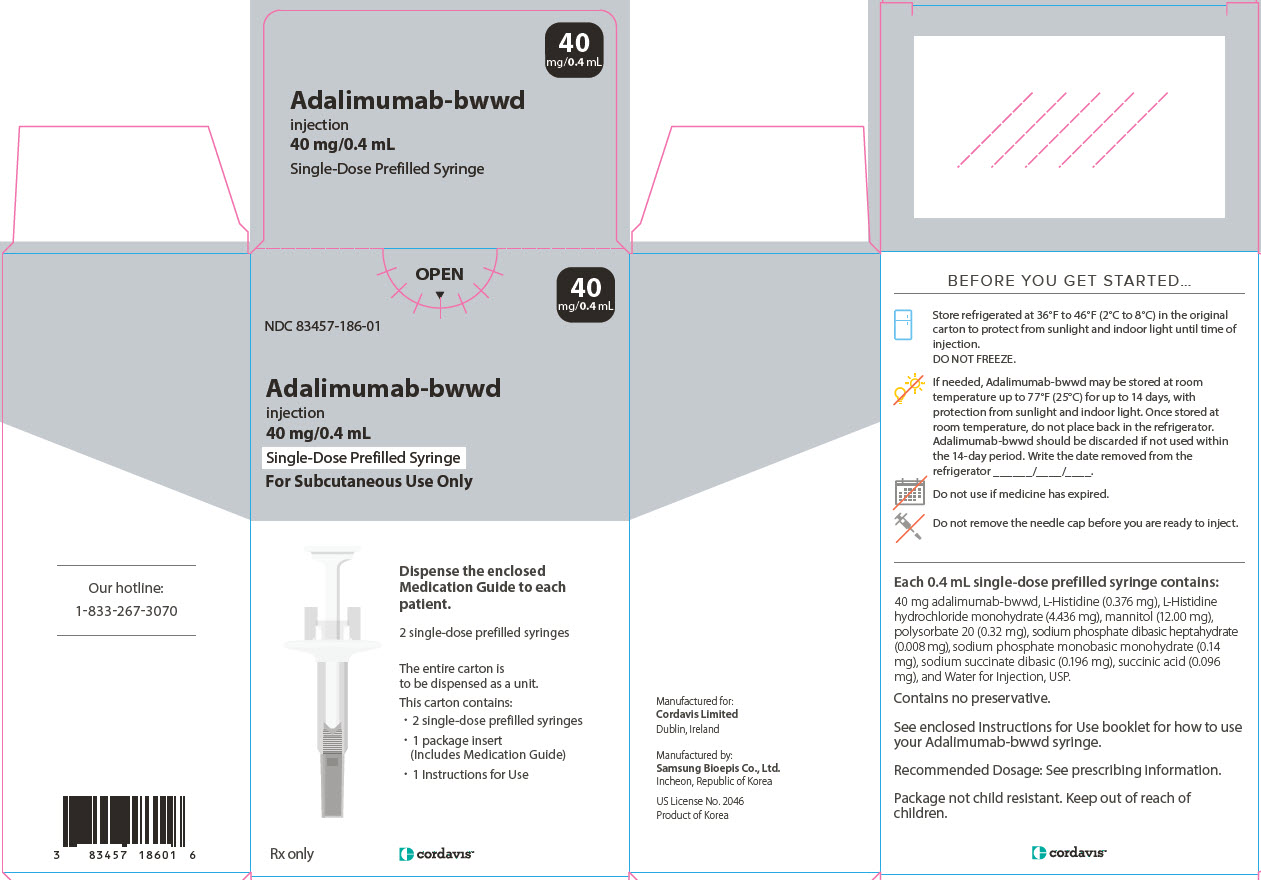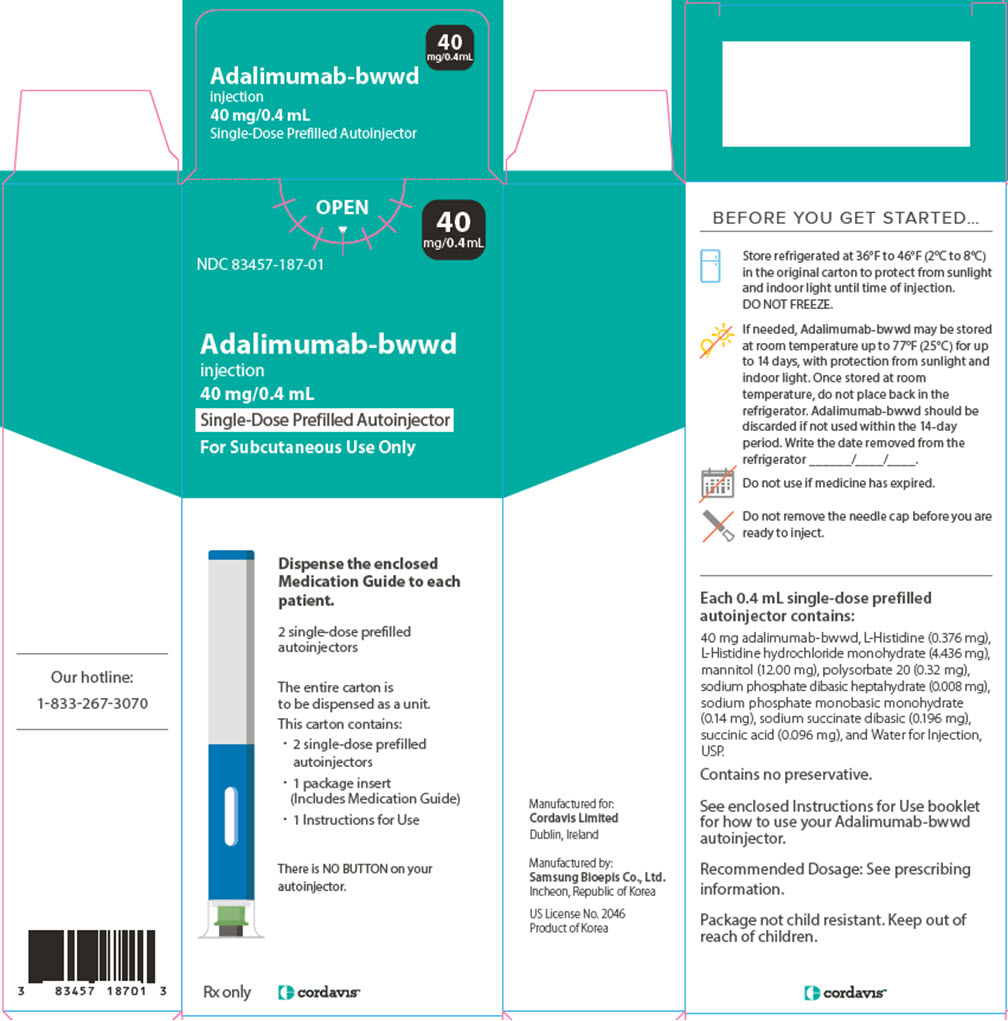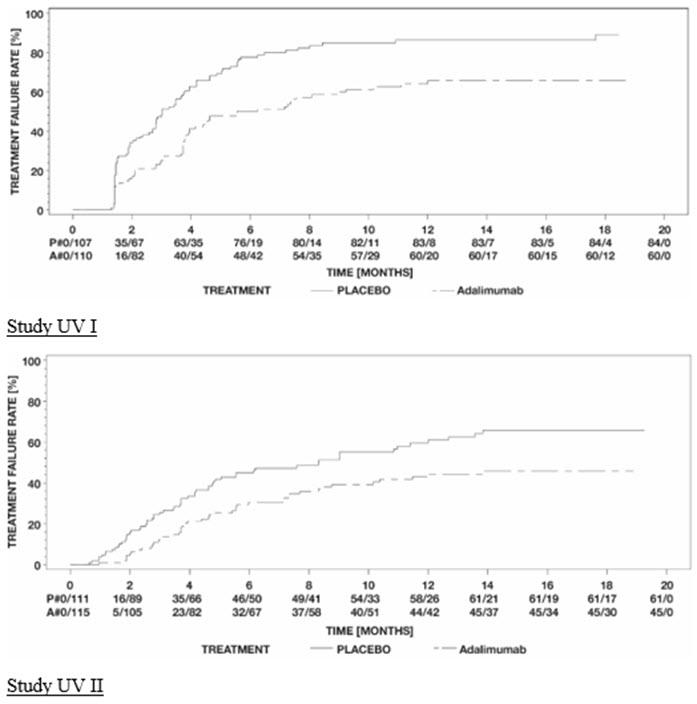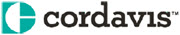 DRUG LABEL: Adalimumab-bwwd
NDC: 83457-186 | Form: SOLUTION
Manufacturer: Cordavis Limited
Category: prescription | Type: HUMAN PRESCRIPTION DRUG LABEL
Date: 20251017

ACTIVE INGREDIENTS: ADALIMUMAB 40 mg/0.4 mL
INACTIVE INGREDIENTS: SODIUM PHOSPHATE, MONOBASIC, MONOHYDRATE; SODIUM SUCCINATE ANHYDROUS; SUCCINIC ACID; HISTIDINE; HISTIDINE HYDROCHLORIDE MONOHYDRATE; MANNITOL; POLYSORBATE 20; SODIUM PHOSPHATE, DIBASIC, HEPTAHYDRATE

HIGHLIGHTS OF PRESCRIBING INFORMATION

These highlights do not include all the information needed to use ADALIMUMAB-BWWD safely and effectively. See full prescribing information for ADALIMUMAB-BWWD.
ADALIMUMAB-BWWD injection, for subcutaneous use
Initial U.S. Approval: 2019
Adalimumab-bwwd is biosimilar [Biosimilar means that the biological product is approved based on data demonstrating that it is highly similar to an FDA-approved biological product, known as a reference product, and that there are no clinically meaningful differences between the biosimilar product and the reference product. Biosimilarity of Adalimumab-bwwd has been demonstrated for the condition(s) of use (e.g. indication(s), dosing regimen(s)), strength(s), dosage form(s), and route(s) of administration described in its Full Prescribing Information.] to HUMIRA (adalimumab)

RECENT MAJOR CHANGES

Warnings and Precautions, Autoimmunity (5.9) 10/2025

WARNING: SERIOUS INFECTIONS and MALIGNANCY

See full prescribing information for complete boxed warning.

SERIOUS INFECTIONS (5.1, 6.1):

- Increased risk of serious infections leading to hospitalization or death, including tuberculosis (TB), bacterial sepsis, invasive fungal infections (such as histoplasmosis), and infections due to other opportunistic pathogens.
- Discontinue Adalimumab-bwwd if a patient develops a serious infection or sepsis during treatment.
- Perform test for latent TB; if positive, start treatment for TB prior to starting Adalimumab-bwwd.
- Monitor all patients for active TB during treatment, even if initial latent TB test is negative.

MALIGNANCY (5.2):

- Lymphoma and other malignancies, some fatal, have been reported in children and adolescent patients treated with TNF blockers including adalimumab products.
- Post-marketing cases of hepatosplenic T-cell lymphoma (HSTCL), a rare type of T-cell lymphoma, have occurred in adolescent and young adults with inflammatory bowel disease treated with TNF blockers including adalimumab products.

1 INDICATIONS AND USAGE

Adalimumab-bwwd is a tumor necrosis factor (TNF) blocker indicated for

- Reducing signs and symptoms, inducing major clinical response, inhibiting the progression of structural damage, and improving physical function in adult patients with moderately to severely active rheumatoid arthritis (1.1).
- Reducing signs and symptoms of moderately to severely active polyarticular juvenile idiopathic arthritis in patients 2 years of age and older (1.2).
- Reducing signs and symptoms, inhibiting the progression of structural damage, and improving physical function in adult patients with active psoriatic arthritis (1.3).
- Reducing signs and symptoms in adult patients with active ankylosing spondylitis (1.4).
- Treatment of moderately to severely active Crohn’s disease in adults and pediatric patients 6 years of age and older (1.5).
- Treatment of moderately to severely active ulcerative colitis in adult patients (1.6).
  Limitations of Use: Effectiveness has not been established in patients who have lost response to or were intolerant to TNF blockers.
- Treatment of adult patients with moderate to severe chronic plaque psoriasis who are candidates for systemic therapy or phototherapy, and when other systemic therapies are medically less appropriate (1.7).
- Treatment of moderate to severe hidradenitis suppurativa in adult patients (1.8)
- Treatment of non-infectious intermediate, posterior, and panuveitis in adult patients (1.9).

2 DOSAGE AND ADMINISTRATION

- Administer by subcutaneous injection (2)

Rheumatoid Arthritis, Psoriatic Arthritis, Ankylosing Spondylitis (2.1):

- Adults: 40 mg every other week.
- Some patients with RA not receiving methotrexate may benefit from increasing the dosage to 40 mg every week or 80 mg every other week.

Juvenile Idiopathic Arthritis (2.2):

Pediatric Weight 2 Years of Age and Older | Recommended Dosage
10 kg (22 lbs) to less than 15 kg (33 lbs) | 10 mg every other week
15 kg (33 lbs) to less than 30 kg (66 lbs) | 20 mg every other week
30 kg (66 lbs) and greater | 40 mg every other week

Crohn's Disease (2.3):

- Adults: 160 mg on Day 1 (given in one day or split over two consecutive days); 80 mg on Day 15; and 40 mg every other week starting on Day 29.
- Pediatric Patients 6 Years of Age and Older:

Pediatric Weight | Recommended Dosage
Pediatric Weight | Days 1 and 15 | Starting on Day 29
17 kg (37 lbs) to less than 40 kg (88 lbs) | Day 1: 80 mg; Day 15: 40 mg | 20 mg every other week
40 kg (88 lbs) and greater | Day 1: 160 mg (single dose or split over two consecutive days); Day 15: 80 mg | 40 mg every other week

Ulcerative Colitis (2.4):

- Adults: 160 mg on Day 1 (given in one day or split over two consecutive days), 80 mg on Day 15 and 40 mg every other week starting on Day 29. Discontinue in patients without evidence of clinical remission by eight weeks (Day 57).

Plaque Psoriasis or Adult Uveitis (2.5):

- Adults: 80 mg initial dose, followed by 40 mg every other week starting one week after initial dose.

Hidradenitis Suppurativa (2.6):

- Adults:
  - Day 1: 160 mg (given in one day or split over two consecutive days)
  - Day 15: 80 mg
  - Day 29 and subsequent doses: 40 mg every week or 80 mg every other week

3 DOSAGE FORMS AND STRENGTHS

Injection:

- Single-dose prefilled autoinjector (Adalimumab-bwwd autoinjector): 40 mg/0.8 mL (3)
- Single-dose prefilled glass syringe: 40 mg/0.8 mL (3)
- Single-dose glass vial for institutional use only: 40 mg/0.8 mL (3)
- Single-dose prefilled autoinjector (Adalimumab-bwwd autoinjector): 40 mg/0.4 mL (3)
- Single-dose prefilled glass syringe: 40 mg/0.4 mL (3)

4 CONTRAINDICATIONS

None (4)

5 WARNINGS AND PRECAUTIONS

- Serious infections: Do not start Adalimumab-bwwd during an active infection. If an infection develops, monitor carefully, and stop Adalimumab-bwwd if infection becomes serious (5.1)
- Invasive fungal infections: For patients who develop a systemic illness on Adalimumab-bwwd, consider empiric antifungal therapy for those who reside or travel to regions where mycoses are endemic (5.1)
- Malignancies: Incidence of malignancies was greater in adalimumab-treated patients than in controls (5.2)
- Anaphylaxis or serious hypersensitivity reactions may occur (5.3)
- Hepatitis B virus reactivation: Monitor HBV carriers during and several months after therapy. If reactivation occurs, stop Adalimumab-bwwd and begin anti- viral therapy (5.4)
- Demyelinating disease: Exacerbation or new onset, may occur (5.5)
- Cytopenias, pancytopenia: Advise patients to seek immediate medical attention if symptoms develop, and consider stopping Adalimumab-bwwd (5.6)
- Heart failure: Worsening or new onset, may occur (5.8)
- Autoimmunity: Stop Adalimumab-bwwd if lupus-like syndrome or autoimmune hepatitis develop (5.9)

6 ADVERSE REACTIONS

Most common adverse reactions (>10%) are: infections (e.g. upper respiratory, sinusitis), injection site reactions, headache and rash (6.1)

To report SUSPECTED ADVERSE REACTIONS, contact Cordavis Limited at 1-833-267-3070 or FDA at 1-800-FDA-1088 or www.fda.gov/medwatch.

7 DRUG INTERACTIONS

- Abatacept: Increased risk of serious infection (5.1, 5.11, 7.2)
- Anakinra: Increased risk of serious infection (5.1, 5.7, 7.2)
- Live vaccines: Avoid use with Adalimumab-bwwd (5.10, 7.3)

FULL PRESCRIBING INFORMATION

WARNING: SERIOUS INFECTIONS and MALIGNANCY

SERIOUS INFECTIONS

Patients treated with adalimumab products including Adalimumab-bwwd, are at increased risk for developing serious infections that may lead to hospitalization or death [see Warnings and Precautions (5.1)]. Most patients who developed these infections were taking concomitant immunosuppressants such as methotrexate or corticosteroids.

Discontinue Adalimumab-bwwd if a patient develops a serious infection or sepsis.

Reported infections include:

- Active tuberculosis (TB), including reactivation of latent TB. Patients with TB have frequently presented with disseminated or extrapulmonary disease. Test patients for latent TB before Adalimumab-bwwd use and during therapy. Initiate treatment for latent TB prior to Adalimumab-bwwd use.
- Invasive fungal infections, including histoplasmosis, coccidioidomycosis, candidiasis, aspergillosis, blastomycosis, and pneumocystosis. Patients with histoplasmosis or other invasive fungal infections may present with disseminated, rather than localized, disease. Antigen and antibody testing for histoplasmosis may be negative in some patients with active infection. Consider empiric anti-fungal therapy in patients at risk for invasive fungal infections who develop severe systemic illness.
- Bacterial, viral and other infections due to opportunistic pathogens, including Legionella and Listeria.

Carefully consider the risks and benefits of treatment with Adalimumab-bwwd prior to initiating therapy in patients with chronic or recurrent infection.

Monitor patients closely for the development of signs and symptoms of infection during and after treatment with Adalimumab-bwwd, including the possible development of TB in patients who tested negative for latent TB infection prior to initiating therapy [see Warnings and Precautions (5.1) and Adverse Reactions (6.1)].

MALIGNANCY

Lymphoma and other malignancies, some fatal, have been reported in children and adolescent patients treated with TNF blockers including adalimumab products [see Warnings and Precautions (5.2)]. Post-marketing cases of hepatosplenic T-cell lymphoma (HSTCL), a rare type of T-cell lymphoma, have been reported in patients treated with TNF blockers including adalimumab products. These cases have had a very aggressive disease course and have been fatal. The majority of reported TNF blocker cases have occurred in patients with Crohn's disease or ulcerative colitis and the majority were in adolescent and young adult males. Almost all these patients had received treatment with azathioprine or 6-mercaptopurine (6–MP) concomitantly with a TNF blocker at or prior to diagnosis. It is uncertain whether the occurrence of HSTCL is related to use of a TNF blocker or a TNF blocker in combination with these other immunosuppressants [see Warnings and Precautions (5.2)].

1 INDICATIONS AND USAGE

1.1 Rheumatoid Arthritis

Adalimumab-bwwd is indicated for reducing signs and symptoms, inducing major clinical response, inhibiting the progression of structural damage, and improving physical function in adult patients with moderately to severely active rheumatoid arthritis. Adalimumab-bwwd can be used alone or in combination with methotrexate or other non-biologic disease-modifying anti-rheumatic drugs (DMARDs).

1.2 Juvenile Idiopathic Arthritis

Adalimumab-bwwd is indicated for reducing signs and symptoms of moderately to severely active polyarticular juvenile idiopathic arthritis in patients 2 years of age and older. Adalimumab-bwwd can be used alone or in combination with methotrexate.

1.3 Psoriatic Arthritis

Adalimumab-bwwd is indicated for reducing signs and symptoms, inhibiting the progression of structural damage, and improving physical function in adult patients with active psoriatic arthritis. Adalimumab-bwwd can be used alone or in combination with non-biologic DMARDs.

1.4 Ankylosing Spondylitis

Adalimumab-bwwd is indicated for reducing signs and symptoms in adult patients with active ankylosing spondylitis.

1.5 Crohn’s Disease

Adalimumab-bwwd is indicated for the treatment of moderately to severely active Crohn’s disease in adults and pediatric patients 6 years of age and older.

1.6 Ulcerative Colitis

Adalimumab-bwwd is indicated for the treatment of moderately to severely active ulcerative colitis in adult patients.

Limitations of Use

The effectiveness of adalimumab products has not been established in patients who have lost response to or were intolerant to TNF blockers [see Clinical Studies (14.7)].

1.7 Plaque Psoriasis

Adalimumab-bwwd is indicated for the treatment of adult patients with moderate to severe chronic plaque psoriasis who are candidates for systemic therapy or phototherapy, and when other systemic therapies are medically less appropriate. Adalimumab-bwwd should only be administered to patients who will be closely monitored and have regular follow-up visits with a physician [see Warnings and Precautions (5)].

1.8 Hidradenitis Suppurativa

Adalimumab-bwwd is indicated for the treatment of moderate to severe hidradenitis suppurativa in adult patients.

1.9 Uveitis

Adalimumab-bwwd is indicated for the treatment of non-infectious intermediate, posterior, and panuveitis in adult patients.

2 DOSAGE AND ADMINISTRATION

2.1 Recommended Tuberculosis Evaluation

Prior to initiating Adalimumab-bwwd and periodically during therapy, evaluate patients for active tuberculosis and test for latent infection [see Warnings and Precautions (5.1)].

2.2 Recommended Dosage in Rheumatoid Arthritis, Psoriatic Arthritis, and Ankylosing Spondylitis

The recommended subcutaneous dosage of Adalimumab-bwwd for adult patients with rheumatoid arthritis (RA), psoriatic arthritis (PsA), or ankylosing spondylitis (AS) [see Indication and Usage (1.1, 1.3, 1.4)] is 40 mg administered every other week. Methotrexate (MTX), other non-biologic DMARDS, glucocorticoids, nonsteroidal anti- inflammatory drugs (NSAIDs), and/or analgesics may be continued during treatment with Adalimumab-bwwd. In the treatment of RA, some patients not taking concomitant MTX may derive additional benefit from increasing the dosage of Adalimumab-bwwd to 40 mg every week or 80 mg every other week.

2.3 Recommended Dosage in Juvenile Idiopathic Arthritis

The recommended subcutaneous dosage of Adalimumab-bwwd for pediatric patients 2 years of age and older with polyarticular juvenile idiopathic arthritis (JIA) [see Indication and Usage (1.2)], based on weight, is shown below. MTX, glucocorticoids, NSAIDs, and/or analgesics may be continued during treatment with Adalimumab-bwwd.

Pediatric Weight (2 Years of Age and older) | Recommended Dosage
10 kg (22 lbs) to less than 15 kg (33 lbs) | 10 mg every other week
15 kg (33 lbs) to less than 30 kg (66 lbs) | 20 mg every other week
30 kg (66 lbs) and greater | 40 mg every other week

The only dosage form for Adalimumab-bwwd that allows weight-based dosing for pediatric patients below 30 kg is the single-dose glass vial for institutional use only.

Adalimumab products have not been studied in patients with polyarticular JIA less than 2 years of age or in patients with a weight below 10 kg.

2.4 Recommended Dosage in Crohn’s Disease

Subcutaneous Adult Dosage Regimen

The recommended subcutaneous dosage of Adalimumab-bwwd for adult patients with moderately to severely active Crohn’s disease (CD) is 160 mg initially on Day 1 (given in one day or split over two consecutive days), followed by 80 mg two weeks later (Day 15). Two weeks later (Day 29) begin a dosage of 40 mg every other week. Aminosalicylates and/or corticosteroids may be continued during treatment with Adalimumab-bwwd. Azathioprine, 6- mercaptopurine (6-MP) [see Warnings and Precautions (5.2)] or MTX may be continued during treatment with Adalimumab-bwwd if necessary.

Subcutaneous Pediatrics Dosage Regimen

The recommended subcutaneous dosage of Adalimumab-bwwd for pediatric patients 6 years of age and older with moderately to severely active Crohn’s disease (CD), based on body weight is shown below:

Pediatric Weight | Recommended Dosage
Pediatric Weight | Days 1 through 15 | Starting on Day 29
17 kg (37 lbs) to; less than 40 kg (88 lbs) | Day 1: 80 mg; Day 15: 40 mg | 20 mg every other week
40 kg (88 lbs) and greater | Day 1: 160 mg (single dose or split over two consecutive days); Day 15: 80 mg | 40 mg every other week

The only dosage form for Adalimumab-bwwd that allows weight-based dosing for pediatric patients below 40 kg is the single-dose glass vial for institutional use only.

2.5 Recommended Dosage in Ulcerative Colitis

Subcutaneous Adult Dosage Regimen

The recommended subcutaneous dosage of Adalimumab-bwwd for adult patients with moderately to severely active ulcerative colitis is 160 mg initially on Day 1 (given in one day or split over two consecutive days), followed by 80 mg two weeks later (Day 15). Two weeks later (Day 29) continue with a dosage of 40 mg every other week.

Discontinue Adalimumab-bwwd in adult patients without evidence of clinical remission by eight weeks (Day 57) of therapy. Aminosalicylates and/or corticosteroids may be continued during treatment with Adalimumab-bwwd. Azathioprine and 6-mercaptopurine (6-MP) [see Warnings and Precautions (5.2)] may be continued during treatment with Adalimumab-bwwd if necessary.

2.6 Recommended Dosage in Plaque Psoriasis or Adults with Uveitis

The recommended subcutaneous dosage of Adalimumab-bwwd for adult patients with plaque psoriasis (Ps) or Uveitis (UV) [see Indication and Usage (1.7, 1.9)] is an initial dose of 80 mg, followed by 40 mg given every other week starting one week after the initial dose. The use of adalimumab products in moderate to severe chronic Ps beyond one year has not been evaluated in controlled clinical studies.

2.7 Recommended Dosage in Hidradenitis Suppurativa

Subcutaneous Adult Dosage Regimen

The recommended subcutaneous dosage of Adalimumab-bwwd for adult patients with moderate to severe hidradenitis suppurativa (HS) is an initial dose of 160 mg (given in one day or split over two consecutive days), followed by 80 mg two weeks later (Day 15). Begin 40 mg weekly or 80 mg every other week dosing two weeks later (Day 29).

2.8 General Considerations for Administration

Adalimumab-bwwd is intended for use under the guidance and supervision of a physician. A patient may self-inject Adalimumab-bwwd or a caregiver may inject Adalimumab-bwwd using either the Adalimumab-bwwd autoinjector or Adalimumab-bwwd prefilled syringe if a physician determines that it is appropriate, and with medical follow-up, as necessary, after proper training in subcutaneous injection technique.

Adalimumab-bwwd autoinjector or prefilled syringe can be taken out of the refrigerator for about 15 to 30 minutes before injecting to allow the liquid to come to room temperature. Do not remove the cap of autoinjector or prefilled syringe while allowing it to reach room temperature.

Carefully inspect the solution in the Adalimumab-bwwd autoinjector, Adalimumab-bwwd prefilled syringe, or Adalimumab-bwwd single-dose institutional use vial for particulate matter and discoloration prior to subcutaneous administration. If particulates and discolorations are noted, do not use the product. Adalimumab-bwwd does not contain preservatives; therefore, discard unused portions of drug remaining from the syringe [see How Supplied/Storage and Handling (16)].

Instruct patients using the Adalimumab-bwwd autoinjector or Adalimumab-bwwd prefilled syringe to inject the full amount in the syringe, according to the directions provided in the Instructions for Use [see Instructions for Use].

Injections should occur at separate sites in the thigh or abdomen. Rotate injection sites and do not give injections into areas where the skin is tender, bruised, red or hard.

If a dose is missed, administer the dose as soon as possible. Thereafter, resume dosing at the regular scheduled time.

The Adalimumab-bwwd single-dose institutional use vial is for administration within an institutional setting only, such as a hospital, physician’s office or clinic. Withdraw the dose using a sterile needle and syringe and administer promptly by a healthcare provider within an institutional setting. Only administer one dose per vial. The vial does not contain preservatives; therefore, discard unused portions.

3 DOSAGE FORMS AND STRENGTHS

Adalimumab-bwwd is a clear to opalescent, and colorless to pale brown solution available as:

- Autoinjector (Adalimumab-bwwd autoinjector)
  Injection: 40 mg/0.8 mL in a single-dose prefilled autoinjector.
  Injection: 40 mg/0.4 mL in a single-dose prefilled autoinjector.
- Prefilled Syringe
  Injection: 40 mg/0.8 mL in a single-dose prefilled glass syringe.
  Injection: 40 mg/0.4 mL in a single-dose prefilled glass syringe.
- Single-Dose Institutional Use Vial
  Injection: 40 mg/0.8 mL in a single-dose, glass vial for institutional use only.

4 CONTRAINDICATIONS

None.

5 WARNINGS AND PRECAUTIONS

5.1 Serious Infections

Patients treated with adalimumab products, including Adalimumab-bwwd, are at increased risk for developing serious infections involving various organ systems and sites that may lead to hospitalization or death. Opportunistic infections due to bacterial, mycobacterial, invasive fungal, viral, parasitic, or other opportunistic pathogens including aspergillosis, blastomycosis, candidiasis, coccidioidomycosis, histoplasmosis, legionellosis, listeriosis, pneumocystosis and tuberculosis have been reported with TNF blockers. Patients have frequently presented with disseminated rather than localized disease.

The concomitant use of a TNF blocker and abatacept or anakinra was associated with a higher risk of serious infections in patients with rheumatoid arthritis (RA); therefore, the concomitant use of Adalimumab-bwwd and these biologic products is not recommended in the treatment of patients with RA [see Warnings and Precautions (5.7, 5.11) and Drug Interactions (7.2)].

Treatment with Adalimumab-bwwd should not be initiated in patients with an active infection, including localized infections. Patients 65 years of age and older, patients with co-morbid conditions and/or patients taking concomitant immunosuppressants (such as corticosteroids or methotrexate), may be at greater risk of infection. Consider the risks and benefits of treatment prior to initiating therapy in patients:

- with chronic or recurrent infection;
- who have been exposed to tuberculosis;
- with a history of an opportunistic infection;
- who have resided or traveled in areas of endemic tuberculosis or endemic mycoses, such as histoplasmosis, coccidioidomycosis, or blastomycosis; or
- with underlying conditions that may predispose them to infection.

Tuberculosis

Cases of reactivation of tuberculosis and new onset tuberculosis infections have been reported in patients receiving adalimumab products, including patients who have previously received treatment for latent or active tuberculosis. Reports included cases of pulmonary and extrapulmonary (i.e., disseminated) tuberculosis. Evaluate patients for tuberculosis risk factors and test for latent infection prior to initiating Adalimumab-bwwd and periodically during therapy.

Treatment of latent tuberculosis infection prior to therapy with TNF blocking agents has been shown to reduce the risk of tuberculosis reactivation during therapy. Prior to initiating Adalimumab-bwwd, assess if treatment for latent tuberculosis is needed; and consider an induration of ≥ 5 mm a positive tuberculin skin test result, even for patients previously vaccinated with Bacille Calmette- Guerin (BCG).

Consider anti-tuberculosis therapy prior to initiation of Adalimumab-bwwd in patients with a past history of latent or active tuberculosis in whom an adequate course of treatment cannot be confirmed, and for patients with a negative test for latent tuberculosis but having risk factors for tuberculosis infection. Despite prophylactic treatment for tuberculosis, cases of reactivated tuberculosis have occurred in patients treated with adalimumab products. Consultation with a physician with expertise in the treatment of tuberculosis is recommended to aid in the decision whether initiating anti- tuberculosis therapy is appropriate for an individual patient.

Strongly consider tuberculosis in the differential diagnosis in patients who develop a new infection during Adalimumab-bwwd treatment, especially in patients who have previously or recently traveled to countries with a high prevalence of tuberculosis, or who have had close contact with a person with active tuberculosis.

Monitoring

Closely monitor patients for the development of signs and symptoms of infection during and after treatment with Adalimumab-bwwd, including the development of tuberculosis in patients who tested negative for latent tuberculosis infection prior to initiating therapy. Tests for latent tuberculosis infection may also be falsely negative while on therapy with Adalimumab-bwwd.

Discontinue Adalimumab-bwwd if a patient develops a serious infection or sepsis. For a patient who develops a new infection during treatment with Adalimumab-bwwd, closely monitor them, perform a prompt and complete diagnostic workup appropriate for an immunocompromised patient, and initiate appropriate antimicrobial therapy.

Invasive Fungal Infections

If patients develop a serious systemic illness and they reside or travel in regions where mycoses are endemic, consider invasive fungal infection in the differential diagnosis. Antigen and antibody testing for histoplasmosis may be negative in some patients with active infection. Consider appropriate empiric antifungal therapy, taking into account both the risk for severe fungal infection and the risks of antifungal therapy, while a diagnostic workup is being performed. To aid in the management of such patients, consider consultation with a physician with expertise in the diagnosis and treatment of invasive fungal infections.

5.2 Malignancies

Consider the risks and benefits of TNF-blocker treatment including Adalimumab-bwwd prior to initiating therapy in patients with a known malignancy other than a successfully treated non-melanoma skin cancer (NMSC) or when considering continuing a TNF blocker in patients who develop a malignancy.

Malignancies in Adults

In the controlled portions of clinical trials of some TNF-blockers, including adalimumab products, more cases of malignancies have been observed among TNF-blocker-treated adult subjects compared to control-treated adult subjects. During the controlled portions of 39 global adalimumab clinical trials in adult patients with rheumatoid arthritis (RA), psoriatic arthritis (PsA), ankylosing spondylitis (AS), Crohn’s disease (CD), ulcerative colitis (UC), plaque psoriasis (Ps), hidradenitis suppurativa (HS), and uveitis (UV), malignancies, other than non-melanoma (basal cell and squamous cell) skin cancer, were observed at a rate (95% confidence interval) of 0.7 (0.48, 1.03) per 100 patient-years among 7973 adalimumab-treated subjects versus a rate of 0.7 (0.41, 1.17) per 100 patient-years among 4848 control-treated subjects (median duration of treatment of 4 months for adalimumab-treated subjects and 4 months for control-treated subjects). In 52 global controlled and uncontrolled clinical trials of adalimumab in adult patients with RA, PsA, AS, CD, UC, Ps, HS, and UV, the most frequently observed malignancies, other than lymphoma and NMSC, were breast, colon, prostate, lung, and melanoma. The malignancies in adalimumab-treated subjects in the controlled and uncontrolled portions of the studies were similar in type and number to what would be expected in the general U.S. population according to the SEER database (adjusted for age, gender, and race).^1

In controlled trials of other TNF blockers in adult patients at higher risk for malignancies (i.e., subjects with COPD with a significant smoking history and cyclophosphamide-treated patients with Wegener’s granulomatosis), a greater portion of malignancies occurred in the TNF blocker group compared to the control group.

Non-Melanoma Skin Cancer

During the controlled portions of 39 global adalimumab clinical trials in adult patients with RA, PsA, AS, CD, UC, Ps, HS, and UV, the rate (95% confidence interval) of NMSC was 0.8 (0.52, 1.09) per 100 patient-years among adalimumab-treated subjects and 0.2 (0.10, 0.59) per 100 patient-years among control-treated subjects. Examine all patients, and in particular patients with a medical history of prior prolonged immunosuppressant therapy or psoriasis patients with a history of PUVA treatment for the presence of NMSC prior to and during treatment with Adalimumab-bwwd.

Lymphoma and Leukemia

In the controlled portions of clinical trials of all the TNF-blockers in adults, more cases of lymphoma have been observed among TNF-blocker-treated subjects compared to control-treated subjects. In the controlled portions of 39 global adalimumab clinical trials in adult patients with RA, PsA, AS, CD, UC, Ps, HS, and UV, 2 lymphomas occurred among 7973 adalimumab-treated subjects versus 1 among 4848 control-treated subjects. In 52 global controlled and uncontrolled clinical trials of adalimumab in adult patients with RA, PsA, AS, CD, UC, Ps, HS, and UV with a median duration of approximately 0.7 years, including 24,605 subjects and over 40,215 patient- years of adalimumab, the observed rate of lymphomas was approximately 0.11 per 100 patient- years. This is approximately 3-fold higher than expected in the general U.S. population according to the SEER database (adjusted for age, gender, and race).^1 Rates of lymphoma in clinical trials of adalimumab cannot be compared to rates of lymphoma in clinical trials of other TNF blockers and may not predict the rates observed in a broader patient population. Patients with RA and other chronic inflammatory diseases, particularly those with highly active disease and/or chronic exposure to immunosuppressant therapies, may be at a higher risk (up to several fold) than the general population for the development of lymphoma, even in the absence of TNF blockers. Post-marketing cases of acute and chronic leukemia have been reported in association with TNF-blocker use in RA and other indications. Even in the absence of TNF-blocker therapy, patients with RA may be at a higher risk (approximately 2-fold) than the general population for the development of leukemia.

Malignancies in Pediatric Patients and Young Adults

Malignancies, some fatal, have been reported among children, adolescents, and young adults who received treatment with TNF-blockers (initiation of therapy ≤ 18 years of age), of which Adalimumab-bwwd is a member. Approximately half the cases were lymphomas, including Hodgkin's and non-Hodgkin's lymphoma. The other cases represented a variety of different malignancies and included rare malignancies usually associated with immunosuppression and malignancies that are not usually observed in children and adolescents. The malignancies occurred after a median of 30 months of therapy (range 1 to 84 months). Most of the patients were receiving concomitant immunosuppressants. These cases were reported post- marketing and are derived from a variety of sources including registries and spontaneous postmarketing reports.

Postmarketing cases of hepatosplenic T-cell lymphoma (HSTCL), a rare type of T-cell lymphoma, have been reported in patients treated with TNF blockers including adalimumab products. These cases have had a very aggressive disease course and have been fatal. The majority of reported TNF blocker cases have occurred in patients with Crohn's disease or ulcerative colitis and the majority were in adolescent and young adult males. Almost all of these patients had received treatment with the immunosuppressants azathioprine or 6-mercaptopurine (6–MP) concomitantly with a TNF blocker at or prior to diagnosis. It is uncertain whether the occurrence of HSTCL is related to use of a TNF blocker or a TNF blocker in combination with these other immunosuppressants. The potential risk with the combination of azathioprine or 6- mercaptopurine and Adalimumab-bwwd should be carefully considered.

5.3 Hypersensitivity Reactions

Anaphylaxis and angioneurotic edema have been reported following administration of adalimumab products. If an anaphylactic or other serious allergic reaction occurs, immediately discontinue administration of Adalimumab-bwwd and institute appropriate therapy. In clinical trials of adalimumab, hypersensitivity reactions (e.g., rash, anaphylactoid reaction, fixed drug reaction, non-specified drug reaction, urticaria) have been observed.

5.4 Hepatitis B Virus Reactivation

Use of TNF blockers, including Adalimumab-bwwd, may increase the risk of reactivation of hepatitis B virus (HBV) in patients who are chronic carriers of this virus. In some instances, HBV reactivation occurring in conjunction with TNF blocker therapy has been fatal. The majority of these reports have occurred in patients concomitantly receiving other medications that suppress the immune system, which may also contribute to HBV reactivation. Evaluate patients at risk for HBV infection for prior evidence of HBV infection before initiating TNF blocker therapy. Exercise caution in prescribing TNF blockers for patients identified as carriers of HBV. Adequate data are not available on the safety or efficacy of treating patients who are carriers of HBV with anti-viral therapy in conjunction with TNF blocker therapy to prevent HBV reactivation. For patients who are carriers of HBV and require treatment with TNF blockers, closely monitor such patients for clinical and laboratory signs of active HBV infection throughout therapy and for several months following termination of therapy. In patients who develop HBV reactivation, stop Adalimumab-bwwd and initiate effective anti-viral therapy with appropriate supportive treatment. The safety of resuming TNF blocker therapy after HBV reactivation is controlled is not known. Therefore, exercise caution when considering resumption of Adalimumab-bwwd therapy in this situation and monitor patients closely.

5.5 Neurologic Reactions

Use of TNF blocking agents, including adalimumab products, has been associated with rare cases of new onset or exacerbation of clinical symptoms and/or radiographic evidence of central nervous system demyelinating disease, including multiple sclerosis (MS) and optic neuritis, and peripheral demyelinating disease, including Guillain-Barré syndrome. Exercise caution in considering the use of Adalimumab-bwwd in patients with preexisting or recent-onset central or peripheral nervous system demyelinating disorders; discontinuation of Adalimumab-bwwd should be considered if any of these disorders develop. There is a known association between intermediate uveitis and central demyelinating disorders.

5.6 Hematological Reactions

Rare reports of pancytopenia including aplastic anemia have been reported with TNF blocking agents. Adverse reactions of the hematologic system, including medically significant cytopenia (e.g., thrombocytopenia, leukopenia) have been infrequently reported with adalimumab products. The causal relationship of these reports to adalimumab products remains unclear. Advise all patients to seek immediate medical attention if they develop signs and symptoms suggestive of blood dyscrasias or infection (e.g., persistent fever, bruising, bleeding, pallor) while on Adalimumab-bwwd. Consider discontinuation of Adalimumab-bwwd therapy in patients with confirmed significant hematologic abnormalities.

5.7 Increased Risk of Infection When Used with Anakinra

Concurrent use of anakinra (an interleukin-1 antagonist) and another TNF-blocker, was associated with a greater proportion of serious infections and neutropenia and no added benefit compared with the TNF-blocker alone in patients with RA. Therefore, the combination of Adalimumab-bwwd and anakinra is not recommended [see Drug Interactions (7.2)].

5.8 Heart Failure

Cases of worsening congestive heart failure (CHF) and new onset CHF have been reported with TNF blockers. Cases of worsening CHF have also been observed with adalimumab products. Adalimumab products have not been formally studied in patients with CHF; however, in clinical trials of another TNF blocker, a higher rate of serious CHF-related adverse reactions was observed. Exercise caution when using Adalimumab-bwwd in patients who have heart failure and monitor them carefully.

5.9 Autoimmunity

Treatment with adalimumab products may result in the formation of autoantibodies and, rarely, in the development of a lupus-like syndrome or autoimmune hepatitis [see Adverse Reactions (6.1, 6.3)]. If a patient develops symptoms and findings suggestive of a lupus-like syndrome or autoimmune hepatitis following treatment with Adalimumab-bwwd, discontinue treatment and evaluate the patient.

5.10 Immunizations

In a placebo-controlled clinical trial of patients with RA, no difference was detected in anti- pneumococcal antibody response between adalimumab and placebo treatment groups when the pneumococcal polysaccharide vaccine and influenza vaccine were administered concurrently with adalimumab. Similar proportions of subjects developed protective levels of anti-influenza antibodies between adalimumab and placebo treatment groups; however, titers in aggregate to influenza antigens were moderately lower in patients receiving adalimumab. The clinical significance of this is unknown. Patients on Adalimumab-bwwd may receive concurrent vaccinations, except for live vaccines. No data are available on the secondary transmission of infection by live vaccines in patients receiving adalimumab products.

It is recommended that pediatric patients, if possible, be brought up to date with all immunizations in agreement with current immunization guidelines prior to initiating Adalimumab-bwwd therapy. Patients on Adalimumab-bwwd may receive concurrent vaccinations, except for live vaccines.

The safety of administering live or live-attenuated vaccines in infants exposed to adalimumab products in utero is unknown. Risks and benefits should be considered prior to vaccinating (live or live- attenuated) exposed infants [see Use in Specific Populations (8.1, 8.4)].

5.11 Increased Risk of Infection When Used with Abatacept

In controlled trials, the concurrent administration of TNF-blockers and abatacept was associated with a greater proportion of serious infections than the use of a TNF-blocker alone; the combination therapy, compared to the use of a TNF-blocker alone, has not demonstrated improved clinical benefit in the treatment of RA. Therefore, the combination of abatacept with TNF-blockers including Adalimumab-bwwd is not recommended [see Drug Interactions (7.2)].

6 ADVERSE REACTIONS

The following clinically significant adverse reactions are described elsewhere in the labeling:

- Serious Infections [see Warnings and Precautions (5.1)]
- Malignancies [see Warnings and Precautions (5.2)]
- Hypersensitivity Reactions [see Warnings and Precautions (5.3)]
- Hepatitis B Virus Reactivation [see Warnings and Precautions (5.4)]
- Neurologic Reactions [see Warnings and Precautions (5.5)]
- Hematological Reactions [see Warnings and Precautions (5.6)]
- Heart Failure [see Warnings and Precautions (5.8)]
- Autoimmunity [see Warnings and Precautions (5.9)]

6.1 Clinical Trials Experience

Because clinical trials are conducted under widely varying conditions, adverse reaction rates observed in the clinical trials of a drug cannot be directly compared to rates in the clinical trials of another drug and may not reflect the rates observed in practice.

The most common adverse reaction with adalimumab was injection site reactions. In placebo- controlled trials, 20% of subjects treated with adalimumab developed injection site reactions (erythema and/or itching, hemorrhage, pain or swelling), compared to 14% of subjects receiving placebo. Most injection site reactions were described as mild and generally did not necessitate drug discontinuation.

The proportion of subjects who discontinued treatment due to adverse reactions during the double-blind, placebo-controlled portion of studies in subjects with RA (i.e., Studies RA-I, RA- II, RA-III and RA-IV) was 7% for subjects taking adalimumab and 4% for placebo-treated subjects. The most common adverse reactions leading to discontinuation of adalimumab in these RA studies were clinical flare reaction (0.7%), rash (0.3%) and pneumonia (0.3%).

Infections

In the controlled portions of the 39 global adalimumab clinical trials in adult subjects with RA, PsA, AS, CD, UC, Ps, HS, and UV, the rate of serious infections was 4.3 per 100 patient-years in 7973 adalimumab-treated subjects versus a rate of 2.9 per 100 patient-years in 4848 control-treated subjects. Serious infections observed included pneumonia, septic arthritis, prosthetic and post- surgical infections, erysipelas, cellulitis, diverticulitis, and pyelonephritis [see Warnings and Precautions (5.1)].

Tuberculosis and Opportunistic Infections

In 52 global controlled and uncontrolled clinical trials in RA, PsA, AS, CD, UC, Ps, HS, and UV, that included 24,605 adalimumab-treated subjects, the rate of reported active tuberculosis was 0.20 per 100 patient-years and the rate of positive PPD conversion was 0.09 per 100 patient-years. In a subgroup of 10,113 U.S. and Canadian adalimumab-treated subjects, the rate of reported active TB was 0.05 per 100 patient-years and the rate of positive PPD conversion was 0.07 per 100 patient- years. These trials included reports of miliary, lymphatic, peritoneal, and pulmonary TB. Most of the TB cases occurred within the first eight months after initiation of therapy and may reflect recrudescence of latent disease. In these global clinical trials, cases of serious opportunistic infections have been reported at an overall rate of 0.05 per 100 patient-years. Some cases of serious opportunistic infections and TB have been fatal [see Warnings and Precautions (5.1)].

Autoantibodies

In the rheumatoid arthritis controlled trials, 12% of subjects treated with adalimumab and 7% of placebo-treated subjects that had negative baseline ANA titers developed positive titers at week 24. Two subjects out of 3046 treated with adalimumab developed clinical signs suggestive of new- onset lupus-like syndrome. The subjects improved following discontinuation of therapy. No subjects developed lupus nephritis or central nervous system symptoms. The impact of long-term treatment with adalimumab products on the development of autoimmune diseases is unknown.

Liver Enzyme Elevations

There have been reports of severe hepatic reactions including acute liver failure in subjects receiving TNF-blockers. In controlled Phase 3 trials of adalimumab (40 mg SC every other week) in subjects with RA, PsA, and AS with control period duration ranging from 4 to 104 weeks, ALT elevations ≥ 3 x ULN occurred in 3.5% of adalimumab-treated subjects and 1.5% of control- treated subjects. Since many of these subjects in these trials were also taking medications that cause liver enzyme elevations (e.g., NSAIDS, MTX), the relationship between adalimumab and the liver enzyme elevations is not clear. In a controlled Phase 3 trial of adalimumab in subjects with polyarticular JIA who were 4 to 17 years, ALT elevations ≥ 3 x ULN occurred in 4.4% of adalimumab-treated subjects and 1.5% of control-treated subjects (ALT more common than AST); liver enzyme test elevations were more frequent among those treated with the combination of adalimumab and MTX than those treated with adalimumab alone. In general, these elevations did not lead to discontinuation of adalimumab treatment. No ALT elevations ≥3 x ULN occurred in the open-label study of adalimumab in subjects with polyarticular JIA who were 2 to <4 years.

In controlled Phase 3 trials of adalimumab (initial doses of 160 mg and 80 mg, or 80 mg and 40 mg on Days 1 and 15, respectively, followed by 40 mg every other week) in adult subjects with Crohn’s Disease with a control period duration ranging from 4 to 52 weeks, ALT elevations ≥ 3 x ULN occurred in 0.9% of adalimumab-treated subjects and 0.9% of control-treated subjects. In the Phase 3 trial of adalimumab in pediatric subjects with Crohn’s disease which evaluated efficacy and safety of two body weight based maintenance dose regimens following body weight based induction therapy up to 52 weeks of treatment, ALT elevations ≥ 3 x ULN occurred in 2.6% (5/192) of subjects, of whom 4 were receiving concomitant immunosuppressants at baseline; none of these subjects discontinued due to abnormalities in ALT tests. In controlled Phase 3 trials of adalimumab (initial doses of 160 mg and 80 mg on Days 1 and 15 respectively, followed by 40 mg every other week) in adult subjects with UC with control period duration ranging from 1 to 52 weeks, ALT elevations ≥3 x ULN occurred in 1.5% of adalimumab-treated subjects and 1.0% of control-treated subjects. In controlled Phase 3 trials of adalimumab (initial dose of 80 mg then 40 mg every other week) in subjects with Ps with control period duration ranging from 12 to 24 weeks, ALT elevations ≥ 3 x ULN occurred in 1.8% of adalimumab-treated subjects and 1.8% of control-treated subjects. In controlled trials of adalimumab (initial doses of 160 mg at Week 0 and 80 mg at Week 2, followed by 40 mg every week starting at Week 4), in subjects with HS with a control period duration ranging from 12 to 16 weeks, ALT elevations ≥ 3 x ULN occurred in 0.3% of adalimumab-treated subjects and 0.6% of control-treated subjects. In controlled trials of adalimumab (initial doses of 80 mg at Week 0 followed by 40 mg every other week starting at Week 1) in adult subjects with uveitis with an exposure of 165.4 PYs and 119.8 PYs in adalimumab-treated and control-treated subjects, respectively, ALT elevations ≥ 3 x ULN occurred in 2.4% of adalimumab-treated subjects and 2.4% of control-treated subjects.

Other Adverse Reactions

Rheumatoid Arthritis Clinical Studies

The data described below reflect exposure to adalimumab in 2468 subjects, including 2073 exposed for 6 months, 1497 exposed for greater than one year and 1380 in adequate and well-controlled studies (Studies RA-I, RA-II, RA-III, and RA-IV). Adalimumab was studied primarily in placebo- controlled trials and in long-term follow up studies for up to 36 months duration. The population had a mean age of 54 years, 77% were female, 91% were Caucasian and had moderately to severely active rheumatoid arthritis. Most subjects received 40 mg adalimumab every other week [see Clinical Studies (14.1)].

Table 1 summarizes reactions reported at a rate of at least 5% in subjects treated with adalimumab 40 mg every other week compared to placebo and with an incidence higher than placebo. In Study RA-III, the types and frequencies of adverse reactions in the second year open-label extension were similar to those observed in the one-year double-blind portion.

Table 1. Adverse Reactions Reported by ≥ 5% of Subjects Treated with Adalimumab During Placebo-Controlled Period of Pooled RA Studies (Studies RA-I, RA-II, RA-III, and RA-IV)
 | Adalimumab 40 mg subcutaneous Every Other Week | Placebo
 | (N=705) | (N=690)
Adverse Reaction (Preferred Term)
Respiratory
Upper respiratory infection | 17% | 13%
Sinusitis | 11% | 9%
Flu syndrome | 7% | 6%
Gastrointestinal
Nausea | 9% | 8%
Abdominal pain | 7% | 4%
Laboratory Tests*
Laboratory test abnormal | 8% | 7%
Hypercholesterolemia | 6% | 4%
Hyperlipidemia | 7% | 5%
Hematuria | 5% | 4%
Alkaline phosphatase increased | 5% | 3%
Other
Headache | 12% | 8%
Rash | 12% | 6%
Accidental injury | 10% | 8%
Injection site reaction ** | 8% | 1%
Back pain | 6% | 4%
Urinary tract infection | 8% | 5%
Hypertension | 5% | 3%
* Laboratory test abnormalities were reported as adverse reactions in European trials
** Does not include injection site erythema, itching, hemorrhage, pain or swelling

Less Common Adverse Reactions in Rheumatoid Arthritis Clinical Studies

Other infrequent serious adverse reactions that do not appear in the Warnings and Precautions or Adverse Reaction sections that occurred at an incidence of less than 5% in adalimumab-treated subjects in RA-I, RA-II, RA-III, and RA-IV were:

Body As A Whole: Pain in extremity, pelvic pain, surgery, thorax pain

Cardiovascular System: Arrhythmia, atrial fibrillation, chest pain, coronary artery disorder, heart arrest, hypertensive encephalopathy, myocardial infarct, palpitation, pericardial effusion, pericarditis, syncope, tachycardia

Digestive System: Cholecystitis, cholelithiasis, esophagitis, gastroenteritis, gastrointestinal hemorrhage, hepatic necrosis, vomiting

Endocrine System: Parathyroid disorder

Hemic And Lymphatic System: Agranulocytosis, polycythemia

Metabolic And Nutritional Disorders: Dehydration, healing abnormal, ketosis, paraproteinemia, peripheral edema

Musculo-Skeletal System: Arthritis, bone disorder, bone fracture (not spontaneous), bone necrosis, joint disorder, muscle cramps, myasthenia, pyogenic arthritis, synovitis, tendon disorder

Neoplasia: Adenoma

Nervous System: Confusion, paresthesia, subdural hematoma, tremor

Respiratory System: Asthma, bronchospasm, dyspnea, lung function decreased, pleural effusion

Special Senses: Cataract

Thrombosis: Thrombosis leg

Urogenital System: Cystitis, kidney calculus, menstrual disorder

Juvenile Idiopathic Arthritis Clinical Studies

In general, the adverse reactions in the adalimumab-treated subjects in the polyarticular juvenile idiopathic arthritis (JIA) trials (Studies JIA-I and JIA-II) [see Clinical Studies (14.2)] were similar in frequency and type to those seen in adult subjects [see Warnings and Precautions (5), Adverse Reactions (6)]. Important findings and differences from adults are discussed in the following paragraphs.

In Study JIA-I, adalimumab was studied in 171 subjects who were 4 to 17 years of age, with polyarticular JIA. Severe adverse reactions reported in the study included neutropenia, streptococcal pharyngitis, increased aminotransferases, herpes zoster, myositis, metrorrhagia, and appendicitis. Serious infections were observed in 4% of subjects within approximately 2 years of initiation of treatment with adalimumab and included cases of herpes simplex, pneumonia, urinary tract infection, pharyngitis, and herpes zoster.

In Study JIA-I, 45% of subjects experienced an infection while receiving adalimumab with or without concomitant MTX in the first 16 weeks of treatment. The types of infections reported in adalimumab-treated subjects were generally similar to those commonly seen in polyarticular JIA subjects who are not treated with TNF blockers. Upon initiation of treatment, the most common adverse reactions occurring in this population treated with adalimumab were injection site pain and injection site reaction (19% and 16%, respectively). A less commonly reported adverse event in subjects receiving adalimumab was granuloma annulare which did not lead to discontinuation of adalimumab treatment.

In the first 48 weeks of treatment in Study JIA-I, non-serious hypersensitivity reactions were seen in approximately 6% of subjects and included primarily localized allergic hypersensitivity reactions and allergic rash.

In Study JIA-I, 10% of subjects treated with adalimumab who had negative baseline anti-dsDNA antibodies developed positive titers after 48 weeks of treatment. No subject developed clinical signs of autoimmunity during the clinical trial.

Approximately 15% of subjects treated with adalimumab developed mild-to-moderate elevations of creatine phosphokinase (CPK) in Study JIA-I. Elevations exceeding 5 times the upper limit of normal were observed in several subjects. CPK concentrations decreased or returned to normal in all subjects. Most subjects were able to continue adalimumab without interruption.

In Study JIA-II, adalimumab was studied in 32 subjects who were 2 to <4 years of age or 4 years of age and older weighing <15 kg with polyarticular JIA. The safety profile for this population was similar to the safety profile seen in subjects 4 to 17 years of age with polyarticular JIA.

In Study JIA-II, 78% of subjects experienced an infection while receiving adalimumab. These included nasopharyngitis, bronchitis, upper respiratory tract infection, otitis media, and were mostly mild to moderate in severity. Serious infections were observed in 9% of subjects receiving adalimumab in the study and included dental caries, rotavirus gastroenteritis, and varicella.

In Study JIA-II, non-serious allergic reactions were observed in 6% of subjects and included intermittent urticaria and rash, which were all mild in severity.

Psoriatic Arthritis and Ankylosing Spondylitis Clinical Studies

Adalimumab has been studied in 395 subjects with psoriatic arthritis (PsA) in two placebo- controlled trials and in an open label study and in 393 subjects with ankylosing spondylitis (AS) in two placebo-controlled studies [see Clinical Studies (14.3, 14.4)]. The safety profile for subjects with PsA and AS treated with adalimumab 40 mg every other week was similar to the safety profile seen in subjects with RA, adalimumab Studies RA-I through IV.

Crohn’s Disease Clinical Studies

Adults: The safety profile of adalimumab in 1478 adult subjects with Crohn’s disease from four placebo- controlled and two open-label extension studies [see Clinical Studies (14.5)] was similar to the safety profile seen in subjects with RA.

Pediatric Patients 6 Years to 17 Years: The safety profile of adalimumab in 192 pediatric subjects from one double-blind study (Study PCD-I) and one open-label extension study [see Clinical Studies (14.6)] was similar to the safety profile seen in adult subjects with Crohn’s disease.

During the 4-week open label induction phase of Study PCD-I, the most common adverse reactions occurring in the pediatric population treated with adalimumab were injection site pain and injection site reaction (6% and 5%, respectively).

A total of 67% of children experienced an infection while receiving adalimumab in Study PCD-I. These included upper respiratory tract infection and nasopharyngitis.

A total of 5% of children experienced a serious infection while receiving adalimumab in Study PCD-I. These included viral infection, device related sepsis (catheter), gastroenteritis, H1N1 influenza, and disseminated histoplasmosis.

In Study PCD-I, allergic reactions were observed in 5% of children which were all non-serious and were primarily localized reactions.

Ulcerative Colitis Clinical Studies

Adults: The safety profile of adalimumab in 1010 adult subjects with ulcerative colitis (UC) from two placebo- controlled studies and one open-label extension study [see Clinical Studies (14.7)] was similar to the safety profile seen in subjects with RA.

Plaque Psoriasis Clinical Studies

Adalimumab has been studied in 1696 subjects with plaque psoriasis (Ps) in placebo-controlled and open-label extension studies [see Clinical Studies (14.8)]. The safety profile for subjects with Ps treated with adalimumab was similar to the safety profile seen in subjects with RA with the following exceptions. In the placebo-controlled portions of the clinical trials in Ps subjects, adalimumab-treated subjects had a higher incidence of arthralgia when compared to controls (3% vs. 1%).

Hidradenitis Suppurativa Clinical Studies

Adalimumab has been studied in 727 subjects with hidradenitis suppurativa (HS) in three placebo- controlled studies and one open-label extension study [see Clinical Studies (14.9)]. The safety profile for subjects with HS treated with adalimumab weekly was consistent with the known safety profile of adalimumab.

Flare of HS, defined as ≥25% increase from baseline in abscesses and inflammatory nodule counts and with a minimum of 2 additional lesions, was documented in 22 (22%) of the 100 subjects who were withdrawn from adalimumab treatment following the primary efficacy timepoint in two studies.

Uveitis Clinical Studies

Adalimumab has been studied in 464 adult subjects with uveitis (UV) in placebo-controlled and open-label extension studies [see Clinical Studies (14.10)]. The safety profile for subjects with UV treated with adalimumab was similar to the safety profile seen in subjects with RA.

6.2 Immunogenicity

As with all therapeutic proteins, there is potential for immunogenicity. The detection of antibody formation is highly dependent on the sensitivity and specificity of the assay. Additionally, the observed incidence of antibody (including neutralizing antibody) positivity in an assay may be influenced by several factors including assay methodology, sample handling, timing of sample collection, concomitant medications, and underlying disease. For these reasons, comparison of the incidence of antibodies in the studies described below with the incidence of antibodies in other studies or to other adalimumab products may be misleading.

There are two assays that have been used to measure anti-adalimumab antibodies. With the ELISA, antibodies to adalimumab could be detected only when serum adalimumab concentrations were < 2 mcg/mL. The ECL assay can detect anti-adalimumab antibody titers independent of adalimumab concentrations in the serum samples. The incidence of anti- adalimumab antibody (AAA) development in patients treated with adalimumab are presented in Table 2.

Table 2: Anti-Adalimumab Antibody Development Determined by ELISA and ECL Assay in Patients Treated with Adalimumab
Indications |  | Study Duration | Anti-Adalimumab Antibody Incidence by ELISA (n/N) |  | Anti-Adalimumab Antibody Incidence by ECL Assay (n/N)
Indications |  | Study Duration | In all patients who received adalimumab | In patients with serum adalimumab concentrations; < 2 mcg/mL
Rheumatoid Arthritisa |  | 6 to 12 months | 5% (58/1062) | NR | NA
Juvenile Idiopathic Arthritis (JIA) | 4 to 17 years of ageb | 48 weeks | 16% (27/171) | NR | NA
Juvenile Idiopathic Arthritis (JIA) | 2 to 4 years of age or ≥ 4 years of age and weighing < 15 kg | 24 weeks | 7% (1/15)c | NR | NA
Psoriatic Arthritisd |  | 48 weekse | 13% (24/178) | NR | NA
Ankylosing Spondylitis |  | 24 weeks | 9% (16/185) | NR | NA
Adult Crohn’s Disease |  | 56 weeks | 3% (7/269) | 8% (7/86) | NA
Pediatric Crohn’s Disease |  | 52 weeks | 3% (6/182) | 10% (6/58) | NA
Adult Ulcerative Colitis |  | 52 weeks | 5% (19/360) | 21% (19/92) | NA
Plaque Psoriasisf |  | Up to 52 weeksg | 8% (77/920) | 21% (77/372) | NA
Hidradenitis Suppurativa |  | 36 weeks | 7% (30/461) | 28% (58/207)h | 61% (272/445)i
Non-infectious Uveitis |  | 52 weeks | 5% (12/249) | 21% (12/57) | 40% (99/249)j
n: number of patients with anti-adalimumab antibody; NR: not reported; NA: Not applicable (not performed)
a In patients receiving concomitant methotrexate (MTX), the incidence of anti-adalimumab antibody was 1% compared to 12% with adalimumab monotherapy
b In patients receiving concomitant MTX, the incidence of anti-adalimumab antibody was 6% compared to 26% with adalimumab monotherapy
c This patient received concomitant MTX
d In patients receiving concomitant MTX, the incidence of antibody development was 7% compared to 1% in RA
e Subjects enrolled after completing 2 previous studies of 24 weeks or 12 weeks of treatments.
f In plaque psoriasis patients who were on adalimumab monotherapy and subsequently withdrawn from the treatment, the rate of antibodies to adalimumab after retreatment was similar to the rate observed prior to withdrawal
g One 12-week Phase 2 study and one 52-week Phase 3 study
h Among subjects in the 2 Phase 3 studies who stopped adalimumab treatment for up to 24 weeks and in whom adalimumab serum levels subsequently declined to <2 mcg/mL (approximately 22% of total subjects studied)
i No apparent association between antibody development and safety was observed
j No correlation of antibody development to safety or efficacy outcomes was observed

Rheumatoid Arthritis and Psoriatic Arthritis: Subjects in Studies RA-I, RA-II, and RA-III were tested at multiple time points for antibodies to adalimumab using the ELISA during the 6- to 12- month period. No apparent correlation of antibody development to adverse reactions was observed. With monotherapy, subjects receiving every other week dosing may develop antibodies more frequently than those receiving weekly dosing. In subjects receiving the recommended dosage of 40 mg every other week as monotherapy, the ACR 20 response was lower among antibody-positive subjects than among antibody-negative subjects. The long-term immunogenicity of adalimumab products is unknown.

6.3 Postmarketing Experience

The following adverse reactions have been identified during post-approval use of adalimumab products. Because these reactions are reported voluntarily from a population of uncertain size, it is not always possible to reliably estimate their frequency or establish a causal relationship to adalimumab products exposure.

Gastrointestinal disorders: Diverticulitis, large bowel perforations including perforations associated with diverticulitis and appendiceal perforations associated with appendicitis, pancreatitis

General disorders and administration site conditions: Pyrexia

Hepato-biliary disorders: Liver failure, hepatitis, autoimmune hepatitis

Immune system disorders: Sarcoidosis

Neoplasms benign, malignant and unspecified (including cysts and polyps): Merkel Cell Carcinoma (neuroendocrine carcinoma of the skin)

Nervous system disorders: Demyelinating disorders (e.g., optic neuritis, Guillain-Barré syndrome), cerebrovascular accident

Respiratory disorders: Interstitial lung disease, including pulmonary fibrosis, pulmonary embolism

Skin reactions: Stevens Johnson Syndrome, cutaneous vasculitis, erythema multiforme, new or worsening psoriasis (all sub-types including pustular and palmoplantar), alopecia, lichenoid skin reaction

Vascular disorders: Systemic vasculitis, deep vein thrombosis

7 DRUG INTERACTIONS

7.1 Methotrexate

Adalimumab has been studied in rheumatoid arthritis (RA) patients taking concomitant methotrexate (MTX). Although MTX reduced the apparent adalimumab clearance, the data do not suggest the need for dose adjustment of either Adalimumab-bwwd or MTX [see Clinical Pharmacology (12.3)].

7.2 Biological Products

In clinical studies in patients with RA, an increased risk of serious infections has been observed with the combination of TNF blockers with anakinra or abatacept, with no added benefit; therefore, use of Adalimumab-bwwd with abatacept or anakinra is not recommended in patients with RA [see Warnings and Precautions (5.7, 5.11)]. A higher rate of serious infections has also been observed in patients with RA treated with rituximab who received subsequent treatment with a TNF blocker. There is insufficient information regarding the concomitant use of Adalimumab-bwwd and other biologic products for the treatment of RA, PsA, AS, CD, UC, Ps, HS and UV. Concomitant administration of Adalimumab-bwwd with other biologic DMARDS (e.g., anakinra and abatacept) or other TNF blockers is not recommended based upon the possible increased risk for infections and other potential pharmacological interactions.

7.3 Live Vaccines

Avoid the use of live vaccines with Adalimumab-bwwd [see Warnings and Precautions (5.10)].

7.4 Cytochrome P450 Substrates

The formation of CYP450 enzymes may be suppressed by increased concentrations of cytokines (e.g., TNFα, IL-6) during chronic inflammation. It is possible for products that antagonize cytokine activity, such as adalimumab products, to influence the formation of CYP450 enzymes. Upon initiation or discontinuation of Adalimumab-bwwd in patients being treated with CYP450 substrates with a narrow therapeutic index, monitoring of the effect (e.g., warfarin) or drug concentration (e.g., cyclosporine or theophylline) is recommended and the individual dose of the drug product may be adjusted as needed.

8 USE IN SPECIFIC POPULATIONS

8.1 Pregnancy

Risk Summary

Available studies with use of adalimumab during pregnancy do not reliably establish an association between adalimumab and major birth defects. Clinical data are available from the Organization of Teratology Information Specialists (OTIS)/MotherToBaby Pregnancy Registry in pregnant women with rheumatoid arthritis (RA) or Crohn’s disease (CD) treated with adalimumab. Registry results showed a rate of 10% for major birth defects with first trimester use of adalimumab in pregnant women with RA or CD and a rate of 7.5% for major birth defects in the disease- matched comparison cohort. The lack of pattern of major birth defects is reassuring and differences between exposure groups may have impacted the occurrence of birth defects (see Data).

Adalimumab is actively transferred across the placenta during the third trimester of pregnancy and may affect immune response in the in-utero exposed infant (see Clinical Considerations). In an embryo-fetal perinatal development study conducted in cynomolgus monkeys, no fetal harm or malformations were observed with intravenous administration of adalimumab during organogenesis and later in gestation, at doses that produced exposures up to approximately 373 times the maximum recommended human dose (MRHD) of 40 mg subcutaneous without methotrexate (see Data).

The estimated background risk of major birth defects and miscarriage for the indicated populations is unknown. All pregnancies have a background risk of birth defect, loss, or other adverse outcomes. In the U.S. general population, the estimated background risk of major birth defects and miscarriage in clinically recognized pregnancies is 2-4% and 15-20%, respectively.

Clinical Considerations

Disease-associated maternal and embryo/fetal risk

Published data suggest that the risk of adverse pregnancy outcomes in women with RA or inflammatory bowel disease (IBD) is associated with increased disease activity. Adverse pregnancy outcomes include preterm delivery (before 37 weeks of gestation), low birth weight (less than 2500 g) infants, and small for gestational age at birth.

Fetal/Neonatal Adverse Reactions

Monoclonal antibodies are increasingly transported across the placenta as pregnancy progresses, with the largest amount transferred during the third trimester [see Data]. Risks and benefits should be considered prior to administering live or live-attenuated vaccines to infants exposed to adalimumab products in utero [see Use in Specific Populations (8.4)].

Data

Human Data

A prospective cohort pregnancy exposure registry conducted by OTIS/MotherToBaby in the U.S. and Canada between 2004 and 2016 compared the risk of major birth defects in live-born infants of 221 women (69 RA, 152 CD) treated with adalimumab during the first trimester and 106 women (74 RA, 32 CD) not treated with adalimumab.

The proportion of major birth defects among live-born infants in the adalimumab-treated and untreated cohorts was 10% (8.7% RA, 10.5% CD) and 7.5% (6.8% RA, 9.4% CD), respectively. The lack of pattern of major birth defects is reassuring and differences between exposure groups may have impacted the occurrence of birth defects. This study cannot reliably establish whether there is an association between adalimumab and major birth defects because of methodological limitations of the registry, including small sample size, the voluntary nature of the study, and the non-randomized design.

In an independent clinical study conducted in ten pregnant women with IBD treated with adalimumab, adalimumab concentrations were measured in maternal serum as well as in cord blood (n=10) and infant serum (n=8) on the day of birth. The last dose of adalimumab was given between 1 and 56 days prior to delivery. Adalimumab concentrations were 0.16-19.7 mcg/mL in cord blood, 4.28-17.7 mcg/mL in infant serum, and 0-16.1 mcg/mL in maternal serum. In all but one case, the cord blood concentration of adalimumab was higher than the maternal serum concentration, suggesting adalimumab actively crosses the placenta. In addition, one infant had serum concentrations at each of the following: 6 weeks (1.94 mcg/mL), 7 weeks (1.31 mcg/mL), 8 weeks (0.93 mcg/mL), and 11 weeks (0.53 mcg/mL), suggesting adalimumab can be detected in the serum of infants exposed in utero for at least 3 months from birth.

Animal Data

In an embryo-fetal perinatal development study, pregnant cynomolgus monkeys received adalimumab from gestation days 20 to 97 at doses that produced exposures up to 373 times that achieved with the MRHD without methotrexate (on an AUC basis with maternal IV doses up to 100 mg/kg/week). Adalimumab did not elicit harm to the fetuses or malformations.

8.2 Lactation

Risk Summary

Limited data from case reports in the published literature describe the presence of adalimumab in human milk at infant doses of 0.1% to 1% of the maternal serum concentration. Published data suggest that the systemic exposure to a breastfed infant is expected to be low because adalimumab is a large molecule and is degraded in the gastrointestinal tract. However, the effects of local exposure in the gastrointestinal tract are unknown. There are no reports of adverse effects of adalimumab products on the breastfed infant and no effects on milk production. The developmental and health benefits of breastfeeding should be considered along with the mother’s clinical need for Adalimumab-bwwd and any potential adverse effects on the breastfed child from Adalimumab-bwwd or from the underlying maternal condition.

8.4 Pediatric Use

The safety and effectiveness of Adalimumab-bwwd have not been established in pediatric patients with psoriatic arthritis, ankylosing spondylitis, or plaque psoriasis.

The safety and effectiveness of Adalimumab-bwwd have been established for:

- reducing signs and symptoms of moderately to severely active polyarticular JIA in pediatric patients 2 years of age and older.
- the treatment of moderately to severely active Crohn’s disease in pediatric patients 6 years of age and older.

Pediatric assessments for Adalimumab-bwwd demonstrate that Adalimumab-bwwd is safe and effective for pediatric patients in indications for which Humira (adalimumab) is approved. However, Adalimumab-bwwd is not approved for such indications due to marketing exclusivity for Humira (adalimumab).

Due to their inhibition of TNFα, adalimumab products administered during pregnancy could affect immune response in the in utero-exposed newborn and infant. Data from eight infants exposed to adalimumab in utero suggest adalimumab crosses the placenta [see Use in Specific Populations (8.1)]. The clinical significance of elevated adalimumab concentrations in infants is unknown. The safety of administering live or live-attenuated vaccines in exposed infants is unknown. Risks and benefits should be considered prior to vaccinating (live or live-attenuated) exposed infants.

Post-marketing cases of lymphoma, including hepatosplenic T-cell lymphoma and other malignancies, some fatal, have been reported among children, adolescents, and young adults who received treatment with TNF-blockers including adalimumab products [see Warnings and Precautions (5.2)].

Juvenile Idiopathic Arthritis

The safety and effectiveness of Adalimumab-bwwd for the treatment of moderately to severely active polyarticular JIA have been established in pediatric patients 2 years of age and older. Use for this indication is supported by evidence from an adequate and well-controlled study (Study JIA) in patients 4 to 17 years of age [see Clinical Studies (14.2)] and a safety study (Study JIA-II) in patients 2 to <4 years of age where the safety profile was similar to patients 4 to 17 years of age [see Adverse Reactions (6.1)]. Adalimumab products have not been studied in patients with polyarticular JIA less than 2 years of age or in patients with a weight below 10 kg.

The safety of adalimumab in pediatric patients in the polyarticular JIA trials was generally similar to that observed in adults with certain exceptions [see Adverse Reactions (6.1)].

The safety and effectiveness of Adalimumab-bwwd have not been established in pediatric patients with JIA less than 2 years of age.

Pediatric Crohn’s Disease

The safety and effectiveness of Adalimumab-bwwd for the treatment of moderately to severely active Crohn’s disease have been established in pediatric patients 6 years of age and older. Use of Adalimumab-bwwd for this indication is supported by evidence from adequate and well-controlled studies in adults with additional data from a randomized, double-blind, 52-week clinical study of two dose concentrations of adalimumab in 192 pediatric patients (6 years to 17 years of age) [see Adverse Reactions (6.1), Clinical Pharmacology (12.2, 12.3), Clinical Studies (14.6)]. The adverse reaction profile in patients 6 years to 17 years of age was similar to adults.

The safety and effectiveness of Adalimumab-bwwd have not been established in pediatric patients with Crohn’s disease less than 6 years of age.

8.5 Geriatric Use

In clinical studies of RA (Studies RA-I, RA-II, RA-III, and RA-IV), a total of 519 RA subjects 65 years of age and older, including 107 subjects 75 years of age and older, received adalimumab in clinical studies RA-I through IV. No overall difference in effectiveness was observed between these subjects and younger adult subjects.

The frequency of serious infection and malignancy among adalimumab treated subjects 65 years of age and older was higher than for those less than 65 years of age. Consider the benefits and risks of Adalimumab-bwwd in patients 65 years of age and older. In patients treated with Adalimumab-bwwd. closely monitor for the development of infection or malignancy [see Warnings and Precautions (5.1, 5.2)].

10 OVERDOSAGE

Doses up to 10 mg/kg have been administered to patients in clinical trials without evidence of dose-limiting toxicities. In case of overdosage, it is recommended that the patient be monitored for any signs or symptoms of adverse reactions or effects and appropriate symptomatic treatment instituted immediately.

Consider contacting the Poison Help line (1-800-222-1222) or medical toxicologist for additional overdose management recommendations.

11 DESCRIPTION

Adalimumab-bwwd is a tumor necrosis factor blocker. Adalimumab-bwwd is a recombinant human IgG1 monoclonal antibody created using phage display technology resulting in an antibody with human derived heavy and light chain variable regions and human IgG1:k constant regions. Adalimumab-bwwd is produced by recombinant DNA technology in a mammalian cell (Chinese Hamster Ovary (CHO)) expression system and is purified by a process that includes specific viral inactivation and removal steps. It consists of 1330 amino acids and has a molecular weight of approximately 148 kilodaltons.

Adalimumab-bwwd injection is supplied as a sterile, preservative-free solution for subcutaneous administration. The drug product is supplied as either a single-dose, prefilled autoinjector (Adalimumab-bwwd autoinjector) or as a single-dose, 1 mL prefilled glass syringe or as a single-dose institutional use vial. Enclosed within the autoinjector is a single-dose, 1 mL prefilled glass syringe. The solution of Adalimumab-bwwd is clear to opalescent, and colorless to pale brown, with a pH of about 5.2.

Each 40 mg/0.8 mL prefilled syringe, autoinjector, or single-dose institutional use vial delivers 0.8 mL (40 mg) of drug product. Each 0.8 mL of Adalimumab-bwwd contains adalimumab-bwwd (40 mg), citric acid monohydrate (0.544 mg), L‑histidine (0.96 mg), L‑histidine hydrochloride monohydrate (8.64 mg), polysorbate 20 (0.64 mg), sodium citrate dihydrate (1.6 mg), sorbitol (20 mg), and Water for Injection, USP.

Each 40 mg/0.4 mL prefilled syringe or autoinjector delivers 0.4 mL (40 mg) of drug product. Each 0.4 mL of Adalimumab-bwwd contains adalimumab-bwwd (40 mg), L‑histidine (0.376 mg), L‑histidine hydrochloride monohydrate (4.436 mg), mannitol (12.00 mg), polysorbate 20 (0.32 mg), sodium phosphate dibasic heptahydrate (0.008 mg), sodium phosphate monobasic monohydrate (0.14 mg), sodium succinate dibasic (0.196 mg), succinic acid (0.096 mg), and Water for Injection, USP.

12 CLINICAL PHARMACOLOGY

12.1 Mechanism of Action

Adalimumab products bind specifically to TNF-alpha and block its interaction with the p55 and p75 cell surface TNF receptors. Adalimumab products also lyse surface TNF expressing cells in vitro in the presence of complement. Adalimumab products do not bind or inactivate lymphotoxin (TNF-beta). TNF is a naturally occurring cytokine that is involved in normal inflammatory and immune responses. Elevated concentrations of TNF are found in the synovial fluid of patients with RA, JIA, PsA, and AS and play an important role in both the pathologic inflammation and the joint destruction that are hallmarks of these diseases. Increased concentrations of TNF are also found in psoriasis plaques. In Ps, treatment with Adalimumab-bwwd may reduce the epidermal thickness and infiltration of inflammatory cells. The relationship between these pharmacodynamic activities and the mechanism(s) by which adalimumab products exert their clinical effects is unknown.

Adalimumab products also modulate biological responses that are induced or regulated by TNF, including changes in the concentrations of adhesion molecules responsible for leukocyte migration (ELAM-1, VCAM-1, and ICAM-1 with an IC50 of 1-2 X 10^-10 M).

12.2 Pharmacodynamics

After treatment with adalimumab, a decrease in concentrations of acute phase reactants of inflammation (C- reactive protein [CRP] and erythrocyte sedimentation rate [ESR]) and serum cytokines (IL-6) was observed compared to baseline in patients with rheumatoid arthritis. A decrease in CRP concentrations was also observed in patients with Crohn’s disease ulcerative colitis, and hidradenitis suppurativa. Serum concentrations of matrix metalloproteinases (MMP-1 and MMP-3) that produce tissue remodeling responsible for cartilage destruction were also decreased after adalimumab administration.

12.3 Pharmacokinetics

The pharmacokinetics of adalimumab were linear over the dose range of 0.5 to 10 mg/kg following administration of a single intravenous dose (adalimumab products are not approved for intravenous use). Following 20, 40, and 80 mg every other week and every week subcutaneous administration, adalimumab mean serum trough concentrations at steady state increased approximately proportionally with dose in RA patients. The mean terminal half-life was approximately 2 weeks, ranging from 10 to 20 days across studies. Healthy subjects and patients with RA displayed similar adalimumab pharmacokinetics.

Adalimumab exposure in patients treated with 80 mg every other week is estimated to be comparable with that in patients treated with 40 mg every week.

Absorption

The average absolute bioavailability of adalimumab following a single 40 mg subcutaneous dose was 64%. The mean time to reach the maximum concentration was 5.5 days (131 ± 56 hours) and the maximum serum concentration was 4.7 ± 1.6 mcg/mL in healthy subjects following a single 40 mg subcutaneous administration of adalimumab.

Distribution

The distribution volume (Vss) ranged from 4.7 to 6.0 L following intravenous administration of doses ranging from 0.25 to 10 mg/kg in RA patients.

Elimination

The single dose pharmacokinetics of adalimumab in RA patients were determined in several studies with intravenous doses ranging from 0.25 to 10 mg/kg. The systemic clearance of adalimumab is approximately 12 mL/hr. In long-term studies with dosing more than two years, there was no evidence of changes in clearance over time in RA patients.

Patient Population

Rheumatoid Arthritis and Ankylosing Spondylitis: In patients receiving 40 mg adalimumab every other week, adalimumab mean steady-state trough concentrations were approximately 5 mcg/mL and 8 to 9 mcg/mL, without and with MTX concomitant treatment, respectively. Adalimumab concentrations in the synovial fluid from five rheumatoid arthritis patients ranged from 31 to 96% of those in serum. The pharmacokinetics of adalimumab in patients with AS were similar to those in patients with RA.

Psoriatic Arthritis: In patients receiving 40 mg every other week, adalimumab mean steady-state trough concentrations were 6 to 10 mcg/mL and 8.5 to 12 mcg/mL, without and with MTX concomitant treatment, respectively.

Plaque Psoriasis: Adalimumab mean steady-state trough concentration was approximately 5 to 6 mcg/mL during adalimumab 40 mg every other week treatment.

Adult Uveitis: Adalimumab mean steady concentration was approximately 8 to 10 mcg/mL during adalimumab 40 mg every other week treatment.

Adult Hidradenitis Suppurativa: Adalimumab trough concentrations were approximately 7 to 8 mcg/mL at Week 2 and Week 4, respectively, after receiving 160 mg on Week 0 followed by 80 mg on Week 2. Mean steady-state trough concentrations at Week 12 through Week 36 were approximately 7 to 11 mcg/mL during adalimumab 40 mg every week treatment.

Adult Crohn’s Disease: Adalimumab mean trough concentrations were approximately 12 mcg/mL at Week 2 and Week 4 after receiving 160 mg on Week 0 followed by 80 mg on Week 2. Mean steady-state trough concentrations were 7 mcg/mL at Week 24 and Week 56 during adalimumab 40 mg every other week treatment.

Adult Ulcerative Colitis: Adalimumab mean trough concentrations were approximately 12 mcg/mL at Week 2 and Week 4 after receiving 160 mg on Week 0 followed by 80 mg on Week 2. Mean steady-state trough concentrations were approximately 8 mcg/mL and 15 mcg/mL at Week 52 after receiving a dose of adalimumab 40 mg every other week and 40 mg every week, respectively.

Anti-Drug Antibody Effects on Pharmacokinetics

Rheumatoid Arthritis: A trend toward higher apparent clearance of adalimumab in the presence of anti-adalimumab antibodies was identified.

Hidradenitis Suppurativa: In subjects with moderate to severe HS, antibodies to adalimumab were associated with reduced serum adalimumab concentrations. In general, the extent of reduction in serum adalimumab concentrations is greater with increasing titers of antibodies to adalimumab.

Specific Populations

Geriatric Patients: A lower clearance with increasing age was observed in patients with RA aged 40 to >75 years.

Pediatric Patients:

Juvenile Idiopathic Arthritis:

- 4 years to 17 years of age: The adalimumab mean steady-state trough concentrations were 6.8 mcg/mL and 10.9 mcg/mL in patients weighing <30 kg receiving 20 mg adalimumab subcutaneously every other week as monotherapy or with concomitant MTX, respectively. The adalimumab mean steady-state trough concentrations were 6.6 mcg/mL and 8.1 mcg/mL in patients weighing ≥30 kg receiving 40 mg adalimumab subcutaneously every other week as monotherapy or with MTX concomitant treatment, respectively.
- 2 years to <4 years of age or 4 years of age and older weighing <15 kg: The adalimumab mean steady-state trough adalimumab concentrations were 6.0 mcg/mL and 7.9 mcg/mL in patients receiving adalimumab subcutaneously every other week as monotherapy or with MTX concomitant treatment, respectively.

Pediatric Crohn's Disease: Adalimumab mean ± SD concentrations were 15.7±6.5 mcg/mL at Week 4 following 160 mg at Week 0 and 80 mg at Week 2, and 10.5±6.0 mcg/mL at Week 52 following 40 mg every other week dosing in patients weighing ≥ 40 kg. Adalimumab mean ± SD concentrations were 10.6±6.1 mcg/mL at Week 4 following dosing 80 mg at Week 0 and 40 mg at Week 2, and 6.9±3.6 mcg/mL at Week 52 following 20 mg every other week dosing in patients weighing < 40 kg.

Male and Female Patients: No gender-related pharmacokinetic differences were observed after correction for a patient’s body weight. Healthy subjects and patients with rheumatoid arthritis displayed similar adalimumab pharmacokinetics.

Patients with Renal or Hepatic Impairment: No pharmacokinetic data are available in patients with hepatic or renal impairment.

Rheumatoid factor or CRP concentrations: Minor increases in apparent clearance were predicted in RA patients receiving doses lower than the recommended dose and in RA patients with high rheumatoid factor or CRP concentrations. These increases are not likely to be clinically important.

Drug Interaction Studies:

Methotrexate: MTX reduced adalimumab apparent clearance after single and multiple dosing by 29% and 44% respectively, in patients with RA [see Drug Interactions (7.1)].

13 NONCLINICAL TOXICOLOGY

13.1 Carcinogenesis, Mutagenesis, Impairment of Fertility

Long-term animal studies of adalimumab products have not been conducted to evaluate the carcinogenic potential or its effect on fertility.

14 CLINICAL STUDIES

14.1 Clinical Studies in Rheumatoid Arthritis

The efficacy and safety of adalimumab were assessed in five randomized, double-blind studies in subjects ≥18 years of age with active rheumatoid arthritis (RA) diagnosed according to American College of Rheumatology (ACR) criteria. Subjects had at least 6 swollen and 9 tender joints. Adalimumab was administered subcutaneously in combination with methotrexate (MTX) (12.5 to 25 mg, Studies RA-I, RA-III and RA-V) or as monotherapy (Studies RA-II and RA-V) or with other disease-modifying anti-rheumatic drugs (DMARDs) (Study RA-IV).

Study RA-I evaluated 271 subjects who had failed therapy with at least one but no more than four DMARDs and had inadequate response to MTX. Doses of 20, 40 or 80 mg of adalimumab or placebo were given every other week for 24 weeks.

Study RA-II evaluated 544 subjects who had failed therapy with at least one DMARD. Doses of placebo, 20 or 40 mg of adalimumab were given as monotherapy every other week or weekly for 26 weeks.

Study RA-III evaluated 619 subjects who had an inadequate response to MTX. Subjects received placebo, 40 mg of adalimumab every other week with placebo injections on alternate weeks, or 20 mg of adalimumab weekly for up to 52 weeks. Study RA-III had an additional primary endpoint at 52 weeks of inhibition of disease progression (as detected by X-ray results). Upon completion of the first 52 weeks, 457 subjects enrolled in an open-label extension phase in which 40 mg of adalimumab was administered every other week for up to 5 years.

Study RA-IV assessed safety in 636 subjects who were either DMARD-naive or were permitted to remain on their pre-existing rheumatologic therapy provided that therapy was stable for a minimum of 28 days. Subjects were randomized to 40 mg of adalimumab or placebo every other week for 24 weeks.

Study RA-V evaluated 799 subjects with moderately to severely active RA of less than 3 years duration who were ≥18 years old and MTX naïve. Subjects were randomized to receive either MTX (optimized to 20 mg/week by week 8), adalimumab 40 mg every other week or adalimumab /MTX combination therapy for 104 weeks. Subjects were evaluated for signs and symptoms, and for radiographic progression of joint damage. The median disease duration among subjects enrolled in the study was 5 months. The median MTX dose achieved was 20 mg.

Clinical Response

The percent of adalimumab treated subjects achieving ACR 20, 50 and 70 responses in Studies RA- II and III are shown in Table 3.

Table 3. ACR Responses in Studies RA-II and RA-III (Percent of Subjects)
 | Study RA-II Monotherapy (26 weeks) |  |  | Study RA-III Methotrexate Combination (24 and 52 weeks)
Response | Placebo | Adalimumab 40 mg every other week | Adalimumab 40 mg weekly | Placebo/MTX | Adalimumab/MTX 40 mg every other week
 | N=110 | N=113 | N=103 | N=200 | N=207
ACR20
Month 6 | 19% | 46%* | 53%* | 30% | 63%*
Month 12 | NA | NA | NA | 24% | 59%*
ACR50
Month 6 | 8% | 22%* | 35%* | 10% | 39%*
Month 12 | NA | NA | NA | 10% | 42%*
ACR70
Month 6 | 2% | 12%* | 18%* | 3% | 21%*
Month 12 | NA | NA | NA | 5% | 23%*
* p<0.01, adalimumab vs. placebo

The results of Study RA-I were similar to Study RA-III; subjects receiving adalimumab 40 mg every other week in Study RA-I also achieved ACR 20, 50 and 70 response rates of 65%, 52% and 24%, respectively, compared to placebo responses of 13%, 7% and 3% respectively, at 6 months (p<0.01).

The results of the components of the ACR response criteria for Studies RA-II and RA-III are shown in Table 4. ACR response rates and improvement in all components of ACR response were maintained to week 104. Over the 2 years in Study RA-III, 20% of adalimumab subjects receiving 40 mg every other week achieved a major clinical response, defined as maintenance of an ACR 70 response over a 6-month period. ACR responses were maintained in similar proportions of subjects for up to 5 years with continuous adalimumab treatment in the open- label portion of Study RA-III.

Table 4. Components of ACR Response in Studies RA-II and RA-III
 | Study RA-II |  |  |  | Study RA-III
Parameter (median) | Placebo N=110 |  | Adalimumaba N=113 |  | Placebo/MTX N=200 |  | Adalimumaba/MTX N=207
 | Baseline | Wk 26 | Baseline | Wk 26 | Baseline | Wk 24 | Baseline | Wk 24
Number of tender joints (0-68) | 35 | 26 | 31 | 16* | 26 | 15 | 24 | 8*
Number of swollen joints (0-66) | 19 | 16 | 18 | 10* | 17 | 11 | 18 | 5*
Physician global assessmentb | 7.0 | 6.1 | 6.6 | 3.7* | 6.3 | 3.5 | 6.5 | 2.0*
Patient global assessmentb | 7.5 | 6.3 | 7.5 | 4.5* | 5.4 | 3.9 | 5.2 | 2.0*
Painb | 7.3 | 6.1 | 7.3 | 4.1* | 6.0 | 3.8 | 5.8 | 2.1*
Disability index (HAQ)c | 2.0 | 1.9 | 1.9 | 1.5* | 1.5 | 1.3 | 1.5 | 0.8*
CRP (mg/dL) | 3.9 | 4.3 | 4.6 | 1.8* | 1.0 | 0.9 | 1.0 | 0.4*
a 40 mg adalimumab administered every other week
b Visual analogue scale; 0 = best, 10 = worst
c Disability Index of the Health Assessment Questionnaire; 0 = best, 3 = worst, measures the patient’s ability to perform the following: dress/groom, arise, eat, walk, reach, grip, maintain hygiene, and maintain daily activity
* p<0.001, adalimumab vs. placebo, based on mean change from baseline

The time course of ACR 20 response for Study RA-III is shown in Figure 1.

In Study RA-III, 85% of subjects with ACR 20 responses at week 24 maintained the response at 52 weeks. The time course of ACR 20 response for Study RA-I and Study RA-II were similar.

Figure 1. Study RA-III ACR 20 Responses over 52 Weeks

In Study RA-IV, 53% of subjects treated with adalimumab 40 mg every other week plus standard of care had an ACR 20 response at week 24 compared to 35% on placebo plus standard of care (p<0.001). No unique adverse reactions related to the combination of adalimumab and other DMARDs were observed.

In Study RA-V with MTX naïve subjects with recent onset RA, the combination treatment with adalimumab plus MTX led to greater percentages of subjects achieving ACR responses than either MTX monotherapy or adalimumab monotherapy at Week 52 and responses were sustained at Week 104 (see Table 5).

Table 5. ACR Response in Study RA-V (Percent of Subjects)
Response | MTXb N=257 | Adalimumabc N=274 | Adalimumab/MTX N=268
ACR20
Week 52 | 63% | 54% | 73%
Week 104 | 56% | 49% | 69%
ACR50
Week 52 | 46% | 41% | 62%
Week 104 | 43% | 37% | 59%
ACR70
Week 52 | 27% | 26% | 46%
Week 104 | 28% | 28% | 47%
Major Clinical Responsea | 28% | 25% | 49%
a Major clinical response is defined as achieving an ACR70 response for a continuous six month period
b p<0.05, adalimumab/MTX vs. MTX for ACR 20
p<0.001, adalimumab/MTX vs. MTX for ACR 50 and 70, and Major Clinical Response
c p<0.001, adalimumab/MTX vs. adalimumab

At Week 52, all individual components of the ACR response criteria for Study RA-V improved in the adalimumab/MTX group and improvements were maintained to Week 104.

Radiographic Response

In Study RA-III, structural joint damage was assessed radiographically and expressed as change in Total Sharp Score (TSS) and its components, the erosion score and Joint Space Narrowing (JSN) score, at month 12 compared to baseline. At baseline, the median TSS was approximately 55 in the placebo and 40 mg every other week groups. The results are shown in Table 6. Adalimumab/MTX treated subjects demonstrated less radiographic progression than subjects receiving MTX alone at 52 weeks.

Table 6. Radiographic Mean Changes Over 12 Months in Study RA-III
 | Placebo/MTX | Adalimumab/MTX 40 mg every other week | Placebo/MTX- Adalimumab/MTX (95% Confidence Interval*) | P-value**
Total Sharp score | 2.7 | 0.1 | 2.6 (1.4, 3.8) | <0.001
Erosion score | 1.6 | 0.0 | 1.6 (0.9, 2.2) | <0.001
JSN score | 1.0 | 0.1 | 0.9 (0.3, 1.4) | 0.002
* 95% confidence intervals for the differences in change scores between MTX and adalimumab.
** Based on rank analysis

In the open-label extension of Study RA-III, 77% of the original subjects treated with any dose of adalimumab were evaluated radiographically at 2 years. Subjects maintained inhibition of structural damage, as measured by the TSS. Fifty-four percent had no progression of structural damage as defined by a change in the TSS of zero or less. Fifty-five percent (55%) of subjects originally treated with 40 mg adalimumab every other week have been evaluated radiographically at 5 years. Subjects had continued inhibition of structural damage with 50% showing no progression of structural damage defined by a change in the TSS of zero or less.

In Study RA-V, structural joint damage was assessed as in Study RA-III. Greater inhibition of radiographic progression, as assessed by changes in TSS, erosion score and JSN was observed in the adalimumab/MTX combination group as compared to either the MTX or adalimumab monotherapy group at Week 52 as well as at Week 104 (see Table 7).

Table 7. Radiographic Mean Change* in Study RA-V
 |  | MTXa N=257 | Adalimumaba,b N=274 | Adalimumab/MTX N=268
52 Weeks | Total Sharp score | 5.7 (4.2, 7.3) | 3.0 (1.7, 4.3) | 1.3 (0.5, 2.1)
 | Erosion score | 3.7 (2.7, 4.8) | 1.7 (1.0, 2.4) | 0.8 (0.4, 1.2)
 | JSN score | 2.0 (1.2, 2.8) | 1.3 (0.5, 2.1) | 0.5 (0.0, 1.0)
104 Weeks | Total Sharp score | 10.4 (7.7, 13.2) | 5.5 (3.6, 7.4) | 1.9 (0.9, 2.9)
 | Erosion score | 6.4 (4.6, 8.2) | 3.0 (2.0, 4.0) | 1.0 (0.4, 1.6)
 | JSN score | 4.1 (2.7, 5.4) | 2.6 (1.5, 3.7) | 0.9 (0.3, 1.5)
* mean (95% confidence interval)
a p<0.001, adalimumab/MTX vs. MTX at 52 and 104 weeks and for adalimumab/MTX vs. adalimumab at 104 weeks
b p<0.01, for adalimumab/MTX vs. adalimumab at 52 weeks

Physical Function Response

In studies RA-I through IV, adalimumab showed significantly greater improvement than placebo in the disability index of Health Assessment Questionnaire (HAQ-DI) from baseline to the end of study, and significantly greater improvement than placebo in the health-outcomes as assessed by The Short Form Health Survey (SF 36). Improvement was seen in both the Physical Component Summary (PCS) and the Mental Component Summary (MCS).

In Study RA-III, the mean (95% CI) improvement in HAQ-DI from baseline at week 52 was 0.60 (0.55, 0.65) for the adalimumab subjects and 0.25 (0.17, 0.33) for placebo/MTX (p<0.001) subjects. Sixty-three percent of adalimumab -treated subjects achieved a 0.5 or greater improvement in HAQ-DI at week 52 in the double-blind portion of the study. Eighty-two percent of these subjects maintained that improvement through week 104 and a similar proportion of subjects maintained this response through week 260 (5 years) of open-label treatment. Mean improvement in the SF-36 was maintained through the end of measurement at week 156 (3 years).

In Study RA-V, the HAQ-DI and the physical component of the SF-36 showed greater improvement (p<0.001) for the adalimumab/MTX combination therapy group versus either the MTX monotherapy or the adalimumab monotherapy group at Week 52, which was maintained through Week 104.

14.2 Clinical Studies in Juvenile Idiopathic Arthritis

The safety and efficacy of adalimumab was assessed in two studies (Studies JIA-I and JIA-II) in subjects with active polyarticular juvenile idiopathic arthritis (JIA).

Study JIA-I

The safety and efficacy of adalimumab were assessed in a multicenter, randomized, withdrawal, double-blind, parallel-group study in 171 subjects who were 4 to 17 years of age with polyarticular JIA. In the study, the subjects were stratified into two groups: MTX-treated or non- MTX-treated. All subjects had to show signs of active moderate or severe disease despite previous treatment with NSAIDs, analgesics, corticosteroids, or DMARDS. Subjects who received prior treatment with any biologic DMARDS were excluded from the study.

The study included four phases: an open-label lead in phase (OL-LI; 16 weeks), a double-blind randomized withdrawal phase (DB; 32 weeks), an open-label extension phase (OLE-BSA; up to 136 weeks), and an open-label fixed dose phase (OLE-FD; 16 weeks). In the first three phases of the study, adalimumab was administered based on body surface area at a dose of 24 mg/m^2 up to a maximum total body dose of 40 mg subcutaneously (SC) every other week. In the OLE-FD phase, the subjects were treated with 20 mg of adalimumab SC every other week if their weight was less than 30 kg and with 40 mg of adalimumab SC every other week if their weight was 30 kg or greater. Subjects remained on stable doses of NSAIDs and or prednisone (≤0.2 mg/kg/day or 10 mg/day maximum).

Subjects demonstrating a Pediatric ACR 30 response at the end of OL-LI phase were randomized into the double blind (DB) phase of the study and received either adalimumab or placebo every other week for 32 weeks or until disease flare. Disease flare was defined as a worsening of ≥30% from baseline in ≥3 of 6 Pediatric ACR core criteria, ≥2 active joints, and improvement of >30% in no more than 1 of the 6 criteria. After 32 weeks or at the time of disease flare during the DB phase, subjects were treated in the open-label extension phase based on the BSA regimen (OLE- BSA), before converting to a fixed dose regimen based on body weight (OLE-FD phase).

Study JIA-I Clinical Response

At the end of the 16-week OL-LI phase, 94% of the subjects in the MTX stratum and 74% of the subjects in the non-MTX stratum were Pediatric ACR 30 responders. In the DB phase significantly fewer subjects who received adalimumab experienced disease flare compared to placebo, both without MTX (43% vs. 71%) and with MTX (37% vs. 65%). More subjects treated with adalimumab continued to show pediatric ACR 30/50/70 responses at Week 48 compared to subjects treated with placebo. Pediatric ACR responses were maintained for up to two years in the OLE phase in subjects who received adalimumab throughout the study.

Study JIA-II

Adalimumab was assessed in an open-label, multicenter study in 32 subjects who were 2 to <4 years of age or 4 years of age and older weighing <15 kg with moderately to severely active polyarticular JIA. Most subjects (97%) received at least 24 weeks of adalimumab treatment dosed 24 mg/m^2 up to a maximum of 20 mg every other week as a single SC injection up to a maximum of 120 weeks duration. During the study, most subjects used concomitant MTX, with fewer reporting use of corticosteroids or NSAIDs. The primary objective of the study was evaluation of safety [see Adverse Reactions (6.1)].

14.3 Clinical Studies in Psoriatic Arthritis

The safety and efficacy of adalimumab was assessed in two randomized, double-blind, placebo controlled studies in 413 subjects with psoriatic arthritis (PsA). Upon completion of both studies, 383 subjects enrolled in an open-label extension study, in which 40 mg adalimumab was administered every other week.

Study PsA-I enrolled 313 adult subjects with moderately to severely active PsA (>3 swollen and >3 tender joints) who had an inadequate response to NSAID therapy in one of the following forms: (1) distal interphalangeal (DIP) involvement (N=23); (2) polyarticular arthritis (absence of rheumatoid nodules and presence of plaque psoriasis) (N=210); (3) arthritis mutilans (N=1); (4) asymmetric PsA (N=77); or (5) AS-like (N=2). Subjects on MTX therapy (158 of 313 subjects) at enrollment (stable dose of ≤30 mg/week for >1 month) could continue MTX at the same dose. Doses of adalimumab 40 mg or placebo every other week were administered during the 24-week double-blind period of the study.

Compared to placebo, treatment with adalimumab resulted in improvements in the measures of disease activity (see Table 8 and Table 9). Among subjects with PsA who received adalimumab, the clinical responses were apparent in some subjects at the time of the first visit (two weeks) and were maintained up to 88 weeks in the ongoing open-label study. Similar responses were seen in subjects with each of the subtypes of psoriatic arthritis, although few subjects were enrolled with the arthritis mutilans and ankylosing spondylitis-like subtypes. Responses were similar in subjects who were or were not receiving concomitant MTX therapy at baseline.

Subjects with psoriatic involvement of at least three percent body surface area (BSA) were evaluated for Psoriatic Area and Severity Index (PASI) responses. At 24 weeks, the proportions of subjects achieving a 75% or 90% improvement in the PASI were 59% and 42% respectively, in the adalimumab group (N=69), compared to 1% and 0% respectively, in the placebo group (N=69) (p<0.001). PASI responses were apparent in some subjects at the time of the first visit (two weeks). Responses were similar in subjects who were or were not receiving concomitant MTX therapy at baseline.

Table 8. ACR Response in Study PsA-I (Percent of Subjects)
 | Placebo N=162 | Adalimumab* N=151
ACR20
Week 12 | 14% | 58%
Week 24 | 15% | 57%
ACR50
Week 12 | 4% | 36%
Week 24 | 6% | 39%
ACR70
Week 12 | 1% | 20%
Week 24 | 1% | 23%
* p<0.001 for all comparisons between adalimumab and placebo

Table 9. Components of Disease Activity in Study PsA-I
 | Placebo N= 162 |  | Adalimumab* N=151
Parameter: median | Baseline | 24 weeks | Baseline | 24 weeks
Number of tender jointsa | 23.0 | 17.0 | 20.0 | 5.0
Number of swollen jointsb | 11.0 | 9.0 | 11.0 | 3.0
Physician global assessmentc | 53.0 | 49.0 | 55.0 | 16.0
Patient global assessmentc | 49.5 | 49.0 | 48.0 | 20.0
Painc | 49.0 | 49.0 | 54.0 | 20.0
Disability index (HAQ)d | 1.0 | 0.9 | 1.0 | 0.4
CRP (mg/dL)e | 0.8 | 0.7 | 0.8 | 0.2
* p<0.001 for adalimumab vs. placebo comparisons based on median changes
a Scale 0-78
b Scale 0-76
c Visual analog scale; 0=best, 100=worst
d Disability Index of the Health Assessment Questionnaire; 0=best, 3=worst; measures the patient’s ability to perform the following: dress/groom, arise, eat, walk, reach, grip, maintain hygiene, and maintain daily activity.
e Normal range: 0-0.287 mg/dL

Similar results were seen in an additional, 12-week study in 100 subjects with moderate to severe psoriatic arthritis who had suboptimal response to DMARD therapy as manifested by ≥3 tender joints and ≥3 swollen joints at enrollment.

Radiographic Response

Radiographic changes were assessed in the PsA studies. Radiographs of hands, wrists, and feet were obtained at baseline and Week 24 during the double-blind period when subjects were on adalimumab or placebo and at Week 48 when all subjects were on open-label adalimumab. A modified Total Sharp Score (mTSS), which included distal interphalangeal joints (i.e., not identical to the TSS used for rheumatoid arthritis), was used by readers blinded to treatment group to assess the radiographs.

Adalimumab-treated subjects demonstrated greater inhibition of radiographic progression compared to placebo-treated subjects and this effect was maintained at 48 weeks (see Table 10).

Table 10. Change in Modified Total Sharp Score in Psoriatic Arthritis
 | Placebo N=141 | Adalimumab N=133
 | Week 24 | Week 24 | Week 48
Baseline mean | 22.1 | 23.4 | 23.4
Mean Change ± SD | 0.9 ± 3.1 | -0.1 ± 1.7 | -0.2 ± 4.9*
* <0.001 for the difference between adalimumab, Week 48 and Placebo, Week 24 (primary analysis)

Physical Function Response

In Study PsA-I, physical function and disability were assessed using the HAQ Disability Index (HAQ-DI) and the SF-36 Health Survey. Subjects treated with 40 mg of adalimumab every other week showed greater improvement from baseline in the HAQ-DI score (mean decreases of 47% and 49% at Weeks 12 and 24 respectively) in comparison to placebo (mean decreases of 1% and 3% at Weeks 12 and 24 respectively). At Weeks 12 and 24, subjects treated with adalimumab showed greater improvement from baseline in the SF-36 Physical Component Summary score compared to subjects treated with placebo, and no worsening in the SF-36 Mental Component Summary score. Improvement in physical function based on the HAQ-DI was maintained for up to 84 weeks through the open-label portion of the study.

14.4 Clinical Studies in Ankylosing Spondylitis

The safety and efficacy of adalimumab 40 mg every other week was assessed in 315 adult subjects in a randomized, 24 week double-blind, placebo-controlled study in subjects with active ankylosing spondylitis (AS) who had an inadequate response to glucocorticoids, NSAIDs, analgesics, methotrexate or sulfasalazine. Active AS was defined as subjects who fulfilled at least two of the following three criteria: (1) a Bath AS disease activity index (BASDAI) score ≥4 cm, (2) a visual analog score (VAS) for total back pain ≥ 40 mm, and (3) morning stiffness ≥ 1 hour. The blinded period was followed by an open-label period during which subjects received adalimumab 40 mg every other week subcutaneously for up to an additional 28 weeks.

Improvement in measures of disease activity was first observed at Week 2 and maintained through 24 weeks as shown in Figure 2 and Table 11.

Responses of subjects with total spinal ankylosis (n=11) were similar to those without total ankylosis.

Figure 2. ASAS 20 Response By Visit, Study AS-I

At 12 weeks, the ASAS 20/50/70 responses were achieved by 58%, 38%, and 23%, respectively, of subjects receiving adalimumab, compared to 21%, 10%, and 5% respectively, of subjects receiving placebo (p <0.001). Similar responses were seen at Week 24 and were sustained in subjects receiving open-label adalimumab for up to 52 weeks.

A greater proportion of subjects treated with adalimumab (22%) achieved a low level of disease activity at 24 weeks (defined as a value <20 [on a scale of 0 to 100 mm] in each of the four ASAS response parameters) compared to subjects treated with placebo (6%).

Table 11. Components of Ankylosing Spondylitis Disease Activity
 | Placebo N=107 |  | Adalimumab N=208
 | Baseline mean | Week 24 mean | Baseline mean | Week 24 mean
ASAS 20 Response Criteria*
Patient’s Global Assessment of Disease Activitya* | 65 | 60 | 63 | 38
Total back pain* | 67 | 58 | 65 | 37
Inflammationb* | 6.7 | 5.6 | 6.7 | 3.6
BASFIc* | 56 | 51 | 52 | 34
BASDAId score* | 6.3 | 5.5 | 6.3 | 3.7
BASMIe score* | 4.2 | 4.1 | 3.8 | 3.3
Tragus to wall (cm) | 15.9 | 15.8 | 15.8 | 15.4
Lumbar flexion (cm) | 4.1 | 4.0 | 4.2 | 4.4
Cervical rotation (degrees) | 42.2 | 42.1 | 48.4 | 51.6
Lumbar side flexion (cm) | 8.9 | 9.0 | 9.7 | 11.7
Intermalleolar distance (cm) | 92.9 | 94.0 | 93.5 | 100.8
CRPf* | 2.2 | 2.0 | 1.8 | 0.6
a Percent of subjects with at least a 20% and 10-unit improvement measured on a Visual Analog Scale (VAS) with 0 = “none” and 100 = “severe”
b mean of questions 5 and 6 of BASDAI (defined in ‘d’)
c Bath Ankylosing Spondylitis Functional Index
d Bath Ankylosing Spondylitis Disease Activity Index
e Bath Ankylosing Spondylitis Metrology Index
f C-Reactive Protein (mg/dL)
* statistically significant for comparisons between adalimumab and placebo at Week 24

A second randomized, multicenter, double-blind, placebo-controlled study of 82 subjects with ankylosing spondylitis showed similar results.

Subjects treated with adalimumab achieved improvement from baseline in the Ankylosing Spondylitis Quality of Life Questionnaire (ASQoL) score (-3.6 vs. -1.1) and in the Short Form Health Survey (SF-36) Physical Component Summary (PCS) score (7.4 vs. 1.9) compared to placebo-treated subjects at Week 24.

14.5 Clinical Studies in Adult Crohn’s Disease

The safety and efficacy of multiple doses of adalimumab were assessed in adult subjects with moderately to severely active Crohn’s disease, CD, (Crohn’s Disease Activity Index (CDAI) ≥ 220 and ≤ 450) in randomized, double-blind, placebo-controlled studies. Concomitant stable doses of aminosalicylates, corticosteroids, and/or immunomodulatory agents were permitted, and 79% of subjects continued to receive at least one of these medications.

Induction of clinical remission (defined as CDAI < 150) was evaluated in two studies. In Study CD-I, 299 TNF-blocker naïve subjects were randomized to one of four treatment groups: the placebo group received placebo at Weeks 0 and 2, the 160/80 group received 160 mg adalimumab at Week 0 and 80 mg at Week 2, the 80/40 group received 80 mg at Week 0 and 40 mg at Week 2, and the 40/20 group received 40 mg at Week 0 and 20 mg at Week 2. Clinical results were assessed at Week 4.

In the second induction study, Study CD-II, 325 subjects who had lost response to, or were intolerant to, previous infliximab therapy were randomized to receive either 160 mg adalimumab at Week 0 and 80 mg at Week 2, or placebo at Weeks 0 and 2. Clinical results were assessed at Week 4.

Maintenance of clinical remission was evaluated in Study CD-III. In this study, 854 subjects with active disease received open-label adalimumab, 80 mg at week 0 and 40 mg at Week 2. Subjects were then randomized at Week 4 to 40 mg adalimumab every other week, 40 mg adalimumab every week, or placebo. The total study duration was 56 weeks. Subjects in clinical response (decrease in CDAI ≥70) at Week 4 were stratified and analyzed separately from those not in clinical response at Week 4.

Induction of Clinical Remission

A greater percentage of the subjects treated with 160/80 mg adalimumab achieved induction of clinical remission versus placebo at Week 4 regardless of whether the subjects were TNF blocker naïve (CD-I), or had lost response to or were intolerant to infliximab (CD-II) (see Table 12).

Table 12. Induction of Clinical Remission in Studies CD-I and CD-II (Percent of Subjects)
 | CD-I |  | CD-II
 | Placebo N=74 | Adalimumab 160/80 mg N=76 | Placebo N=166 | Adalimumab 160/80 mg N=159
Week 4
Clinical remission | 12% | 36%* | 7% | 21%*
Clinical response | 34% | 58%** | 34% | 52%**
Clinical remission is CDAI score < 150; clinical response is decrease in CDAI of at least 70 points.
* p<0.001 for adalimumab vs. placebo pairwise comparison of proportions
** p<0.01 for adalimumab vs. placebo pairwise comparison of proportions

Maintenance of Clinical Remission

In Study CD-III at Week 4, 58% (499/854) of subjects were in clinical response and were assessed in the primary analysis. At Weeks 26 and 56, greater proportions of subjects who were in clinical response at Week 4 achieved clinical remission in the adalimumab 40 mg every other week maintenance group compared to subjects in the placebo maintenance group (see Table 13). The group that received adalimumab therapy every week did not demonstrate significantly higher remission rates compared to the group that received adalimumab every other week.

Table 13. Maintenance of Clinical Remission in CD-III (Percent of Subjects)
 | Placebo | 40 mg Adalimumab every other week
 | N=170 | N=172
Week 26
Clinical remission | 17% | 40%*
Clinical response | 28% | 54%*
Week 56
Clinical remission | 12% | 36%*
Clinical response | 18% | 43%*
Clinical remission is CDAI score < 150; clinical response is decrease in CDAI of at least 70 points.
* p<0.001 for adalimumab vs. placebo pairwise comparisons of proportions

Of those in response at Week 4 who attained remission during the study, subjects in the adalimumab every other week group maintained remission for a longer time than subjects in the placebo maintenance group. Among subjects who were not in response by Week 12, therapy continued beyond 12 weeks did not result in significantly more responses.

14.6 Clinical Studies in Pediatric Subjects with Crohn’s Disease

A randomized, double-blind, 52-week clinical study of 2 dose concentrations of adalimumab (Study PCD-I) was conducted in 192 pediatric subjects (6 to 17 years of age) with moderately to severely active Crohn’s disease (defined as Pediatric Crohn’s Disease Activity Index (PCDAI) score > 30). Enrolled subjects had over the previous two year period an inadequate response to corticosteroids or an immunomodulator (i.e., azathioprine, 6-mercaptopurine, or methotrexate). Subjects who had previously received a TNF blocker were allowed to enroll if they had previously had loss of response or intolerance to that TNF blocker.

Subjects received open-label induction therapy at a dose based on their body weight (≥40 kg and <40 kg). Subjects weighing ≥40 kg received 160 mg (at Week 0) and 80 mg (at Week 2). Subjects weighing <40 kg received 80 mg (at Week 0) and 40 mg (at Week 2). At Week 4, subjects within each body weight category (≥40 kg and <40 kg) were randomized 1:1 to one of two maintenance dose regimens (high dose and low dose). The high dose was 40 mg every other week for subjects weighing ≥40 kg and 20 mg every other week for subjects weighing <40 kg. The low dose was 20 mg every other week for subjects weighing ≥40 kg and 10 mg every other week for subjects weighing <40 kg.

Concomitant stable dosages of corticosteroids (prednisone dosage ≤40 mg/day or equivalent) and immunomodulators (azathioprine, 6-mercaptopurine, or methotrexate) were permitted throughout the study.

At Week 12, subjects who experienced a disease flare (increase in PCDAI of ≥ 15 from Week 4 and absolute PCDAI > 30) or who were non-responders (did not achieve a decrease in the PCDAI of ≥ 15 from baseline for 2 consecutive visits at least 2 weeks apart) were allowed to dose-escalate (i.e., switch from blinded every other week dosing to blinded every week dosing); subjects who dose-escalated were considered treatment failures.

At baseline, 38% of subjects were receiving corticosteroids, and 62% of subjects were receiving an immunomodulator. Forty-four percent (44%) of subjects had previously lost response or were intolerant to a TNF blocker. The median baseline PCDAI score was 40.

Of the 192 subjects total, 188 subjects completed the 4 week induction period, 152 subjects completed 26 weeks of treatment, and 124 subjects completed 52 weeks of treatment. Fifty-one percent (51%) (48/95) of subjects in the low maintenance dose group dose-escalated, and 38% (35/93) of subjects in the high maintenance dose group dose-escalated.

At Week 4, 28% (52/188) of subjects were in clinical remission (defined as PCDAI ≤ 10).

The proportions of subjects in clinical remission (defined as PCDAI ≤ 10) and clinical response (defined as reduction in PCDAI of at least 15 points from baseline) were assessed at Weeks 26 and 52.

At both Weeks 26 and 52, the proportion of subjects in clinical remission and clinical response was numerically higher in the high dose group compared to the low dose group (Table 14). The recommended maintenance regimen is 20 mg every other week for subjects weighing < 40 kg and 40 mg every other week for subjects weighing ≥ 40 kg. Every week dosing is not the recommended maintenance dosing regimen [see Dosage and Administration (2.3)].

Table 14. Clinical Remission and Clinical Response in Study PCD-I
 | Low Maintenance Dose† (20 or 10 mg every other week); N = 95 | High Maintenance Dose# (40 or 20 mg every other week); N = 93
Week 26
Clinical Remission‡ | 28% | 39%
Clinical Response§ | 48% | 59%
Week 52
Clinical Remission‡ | 23% | 33%
Clinical Response§ | 28% | 42%
†The low maintenance dose was 20 mg every other week for subjects weighing ≥ 40 kg and 10 mg every other week for subjects weighing < 40 kg.
#The high maintenance dose was 40 mg every other week for subjects weighing ≥ 40 kg and 20 mg every other week for subjects weighing < 40 kg.
‡Clinical remission defined as PCDAI ≤ 10.
§Clinical response defined as reduction in PCDAI of at least 15 points from baseline.

14.7 Clinical Studies in Adults with Ulcerative Colitis

The safety and efficacy of adalimumab were assessed in adult subjects with moderately to severely active ulcerative colitis (Mayo score 6 to 12 on a 12 point scale, with an endoscopy subscore of 2 to 3 on a scale of 0 to 3) despite concurrent or prior treatment with immunosuppressants such as corticosteroids, azathioprine, or 6-MP in two randomized, double-blind, placebo-controlled clinical studies (Studies UC-I and UC-II). Both studies enrolled TNF-blocker naïve subjects, but Study UC-II also allowed entry of subjects who lost response to or were intolerant to TNF- blockers. Forty percent (40%) of subjects enrolled in Study UC-II had previously used another TNF-blocker.

Concomitant stable doses of aminosalicylates and immunosuppressants were permitted. In Studies UC-I and II, subjects were receiving aminosalicylates (69%), corticosteroids (59%) and/or azathioprine or 6-MP (37%) at baseline. In both studies, 92% of subjects received at least one of these medications.

Induction of clinical remission (defined as Mayo score ≤ 2 with no individual subscores > 1) at Week 8 was evaluated in both studies. Clinical remission at Week 52 and sustained clinical remission (defined as clinical remission at both Weeks 8 and 52) were evaluated in Study UC-II.

In Study UC-I, 390 TNF-blocker naïve subjects were randomized to one of three treatment groups for the primary efficacy analysis. The placebo group received placebo at Weeks 0, 2, 4 and 6. The 160/80 group received 160 mg adalimumab at Week 0 and 80 mg at Week 2, and the 80/40 group received 80 mg adalimumab at Week 0 and 40 mg at Week 2. After Week 2, subjects in both adalimumab treatment groups received 40 mg every other week.

In Study UC-II, 518 subjects were randomized to receive either adalimumab 160 mg at Week 0, 80 mg at Week 2, and 40 mg every other week starting at Week 4 through Week 50, or placebo starting at Week 0 and every other week through Week 50. Corticosteroid taper was permitted starting at Week 8.

In both Studies UC-I and UC-II, a greater percentage of the subjects treated with 160/80 mg of adalimumab compared to subjects treated with placebo achieved induction of clinical remission. In Study UC-II, a greater percentage of the subjects treated with 160/80 mg of adalimumab compared to subjects treated with placebo achieved sustained clinical remission (clinical remission at both Weeks 8 and 52) (Table 15).

Table 15. Induction of Clinical Remission in Studies UC-I and UC-II and Sustained Clinical Remission in Study UC-II (Percent of Subjects)
 | Study UC-I |  |  | Study UC-II
 | Placebo N=130 | Adalimumab 160/80 mg N=130 | Treatment Difference (95% CI) | Placebo N=246 | Adalimumab 160/80 mg N=248 | Treatment Difference (95% CI)
Induction of Clinical Remission (Clinical Remission at Week 8) | 9.2% | 18.5% | 9.3%* (0.9%, 17.6%) | 9.3% | 16.5% | 7.2%* (1.2%, 12.9%)
Sustained Clinical Remission (Clinical Remission at both Weeks 8 and 52) | N/A | N/A | N/A | 4.1% | 8.5% | 4.4%* (0.1%, 8.6%)
Clinical remission is defined as Mayo score ≤ 2 with no individual subscores > 1.
CI=Confidence interval
* p<0.05 for adalimumab vs. placebo pairwise comparison of proportions

In Study UC-I, there was no statistically significant difference in clinical remission observed between the adalimumab 80/40 mg group and the placebo group at Week 8.

In Study UC-II, 17.3% (43/248) in the adalimumab group were in clinical remission at Week 52 compared to 8.5% (21/246) in the placebo group (treatment difference: 8.8%; 95% confidence interval (CI): [2.8%, 14.5%]; p<0.05).

In the subgroup of subjects in Study UC-II with prior TNF-blocker use, the treatment difference for induction of clinical remission appeared to be lower than that seen in the whole study population, and the treatment differences for sustained clinical remission and clinical remission at Week 52 appeared to be similar to those seen in the whole study population. The subgroup of subjects with prior TNF-blocker use achieved induction of clinical remission at 9% (9/98) in the adalimumab group versus 7% (7/101) in the placebo group, and sustained clinical remission at 5% (5/98) in the adalimumab group versus 1% (1/101) in the placebo group. In the subgroup of subjects with prior TNF-blocker use, 10% (10/98) were in clinical remission at Week 52 in the adalimumab group versus 3% (3/101) in the placebo group.

14.8 Clinical Studies in Plaque Psoriasis

The safety and efficacy of adalimumab were assessed in randomized, double-blind, placebo- controlled studies in 1696 adult subjects with moderate to severe chronic plaque psoriasis (Ps) who were candidates for systemic therapy or phototherapy.

Study Ps-I evaluated 1212 subjects with chronic Ps with ≥10% body surface area (BSA) involvement, Physician’s Global Assessment (PGA) of at least moderate disease severity, and Psoriasis Area and Severity Index (PASI) ≥12 within three treatment periods. In period A, subjects received placebo or adalimumab at an initial dose of 80 mg at Week 0 followed by a dose of 40 mg every other week starting at Week 1. After 16 weeks of therapy, subjects who achieved at least a PASI 75 response at Week 16, defined as a PASI score improvement of at least 75% relative to baseline, entered period B and received open-label 40 mg adalimumab every other week. After 17 weeks of open label therapy, subjects who maintained at least a PASI 75 response at Week 33 and were originally randomized to active therapy in period A were re-randomized in period C to receive 40 mg adalimumab every other week or placebo for an additional 19 weeks. Across all treatment groups the mean baseline PASI score was 19 and the baseline Physician’s Global Assessment score ranged from “moderate” (53%) to “severe” (41%) to “very severe” (6%).

Study Ps-II evaluated 99 subjects randomized to adalimumab and 48 subjects randomized to placebo with chronic plaque psoriasis with ≥10% BSA involvement and PASI ≥12. Subjects received placebo, or an initial dose of 80 mg adalimumab at Week 0 followed by 40 mg every other week starting at Week 1 for 16 weeks. Across all treatment groups the mean baseline PASI score was 21 and the baseline PGA score ranged from “moderate” (41%) to “severe” (51%) to “very severe” (8%).

Studies Ps-I and II evaluated the proportion of subjects who achieved “clear” or “minimal” disease on the 6-point PGA scale and the proportion of subjects who achieved a reduction in PASI score of at least 75% (PASI 75) from baseline at Week 16 (see Table 16 and Table 17).

Additionally, Study Ps-I evaluated the proportion of subjects who maintained a PGA of “clear” or “minimal” disease or a PASI 75 response after Week 33 and on or before Week 52.

Table 16. Efficacy Results at 16 Weeks in Study Ps-I Number of Subjects (%)
 | Adalimumab 40 mg every other week N = 814 | Placebo N = 398
PGA: Clear or minimal* | 506 (62%) | 17 (4%)
PASI 75 | 578 (71%) | 26 (7%)
* Clear = no plaque elevation, no scale, plus or minus hyperpigmentation or diffuse pink or red coloration
Minimal = possible but difficult to ascertain whether there is slight elevation of plaque above normal skin, plus or minus surface dryness with some white coloration, plus or minus up to red coloration

Table 17. Efficacy Results at 16 Weeks in Study Ps-II Number of Subjects (%)
 | Adalimumab 40 mg every other week N = 99 | Placebo N = 48
PGA: Clear or minimal* | 70 (71%) | 5 (10%)
PASI 75 | 77 (78%) | 9 (19%)
* Clear = no plaque elevation, no scale, plus or minus hyperpigmentation or diffuse pink or red coloration
Minimal = possible but difficult to ascertain whether there is slight elevation of plaque above normal skin, plus or minus surface dryness with some white coloration, plus or minus up to red coloration

Additionally, in Study Ps-I, subjects on adalimumab who maintained a PASI 75 were re- randomized to adalimumab (N = 250) or placebo (N = 240) at Week 33. After 52 weeks of treatment with adalimumab, more subjects on adalimumab maintained efficacy when compared to subjects who were re-randomized to placebo based on maintenance of PGA of “clear” or “minimal” disease (68% vs. 28%) or a PASI 75 (79% vs. 43%).

A total of 347 stable responders participated in a withdrawal and retreatment evaluation in an open-label extension study. Median time to relapse (decline to PGA “moderate” or worse) was approximately 5 months. During the withdrawal period, no subject experienced transformation to either pustular or erythrodermic psoriasis. A total of 178 subjects who relapsed re-initiated treatment with 80 mg of adalimumab, then 40 mg every other week beginning at week 1. At week 16, 69% (123/178) of subjects had a response of PGA “clear” or “minimal”.

A randomized, double-blind study (Study Ps-III) compared the efficacy and safety of adalimumab versus placebo in 217 adult subjects. Subjects in the study had to have chronic plaque psoriasis of at least moderate severity on the PGA scale, fingernail involvement of at least moderate severity on a 5-point Physician’s Global Assessment of Fingernail Psoriasis (PGA-F) scale, a Modified Nail Psoriasis Severity Index (mNAPSI) score for the target-fingernail of ≥ 8, and either a BSA involvement of at least 10% or a BSA involvement of at least 5% with a total mNAPSI score for all fingernails of ≥ 20. Subjects received an initial dose of 80 mg adalimumab followed by 40 mg every other week (starting one week after the initial dose) or placebo for 26 weeks followed by open-label adalimumab treatment for an additional 26 weeks. This study evaluated the proportion of subjects who achieved “clear” or “minimal” assessment with at least a 2-grade improvement on the PGA-F scale and the proportion of subjects who achieved at least a 75% improvement from baseline in the mNAPSI score (mNAPSI 75) at Week 26.

At Week 26, a higher proportion of subjects in the adalimumab group than in the placebo group achieved the PGA-F endpoint. Furthermore, a higher proportion of subjects in the adalimumab group than in the placebo group achieved mNAPSI 75 at Week 26 (see Table 18).

Table 18. Efficacy Results at 26 Weeks
Endpoint | Adalimumab 40 mg every other week* N=109 | Placebo N=108
PGA-F: ≥2-grade improvement and clear or minimal | 49% | 7%
mNAPSI 75 | 47% | 3%
* Subjects received 80 mg of adalimumab at Week 0, followed by 40 mg every other week starting at Week 1.

Nail pain was also evaluated and improvement in nail pain was observed in Study Ps-III.

14.9 Clinical Studies in Hidradenitis Suppurativa

Two randomized, double-blind, placebo-controlled studies (Studies HS-I and II) evaluated the safety and efficacy of adalimumab in a total of 633 adult subjects with moderate to severe hidradenitis suppurativa (HS) with Hurley Stage II or III disease and with at least 3 abscesses or inflammatory nodules. In both studies, subjects received placebo or adalimumab at an initial dose of 160 mg at Week 0, 80 mg at Week 2, and 40 mg every week starting at Week 4 and continued through Week 11. Subjects used topical antiseptic wash daily. Concomitant oral antibiotic use was allowed in Study HS-II.

Both studies evaluated Hidradenitis Suppurativa Clinical Response (HiSCR) at Week 12. HiSCR was defined as at least a 50% reduction in total abscess and inflammatory nodule count with no increase in abscess count and no increase in draining fistula count relative to baseline (see Table 19). Reduction in HS-related skin pain was assessed using a Numeric Rating Scale in subjects who entered the study with an initial baseline score of 3 or greater on a 11 point scale.

In both studies, a higher proportion of adalimumab- than placebo-treated subjects achieved HiSCR (see Table 19).

Table 19. Efficacy Results at 12 Weeks in Subjects with Moderate to Severe Hidradenitis Suppurativa
 | HS Study I |  | HS Study II*
 | Placebo | Adalimumab 40 mg Weekly | Placebo | Adalimumab 40 mg Weekly
Hidradenitis Suppurativa Clinical Response (HiSCR) | N = 154; 40 (26%) | N = 153; 64 (42%) | N=163 45 (28%) | N=163 96; (59%)
*19.3% of subjects in Study HS-II continued baseline oral antibiotic therapy during the study.

In both studies, from Week 12 to Week 35 (Period B), subjects who had received adalimumab were re-randomized to 1 of 3 treatment groups (adalimumab 40 mg every week, adalimumab 40 mg every other week, or placebo). Subjects who had been randomized to placebo were assigned to receive adalimumab 40 mg every week (Study HS-I) or placebo (Study HS-II).

During Period B, flare of HS, defined as ≥25% increase from baseline in abscesses and inflammatory nodule counts and with a minimum of 2 additional lesions, was documented in 22 (22%) of the 100 subjects who were withdrawn from adalimumab treatment following the primary efficacy timepoint in two studies.

14.10 Clinical Studies in Adults with Uveitis

The safety and efficacy of adalimumab were assessed in adult subjects with non-infectious intermediate, posterior and panuveitis excluding subjects with isolated anterior uveitis, in two randomized, double-masked, placebo-controlled studies (UV I and II). Subjects received placebo or adalimumab at an initial dose of 80 mg followed by 40 mg every other week starting one week after the initial dose. The primary efficacy endpoint in both studies was ´time to treatment failure´.

Treatment failure was a multi-component outcome defined as the development of new inflammatory chorioretinal and/or inflammatory retinal vascular lesions, an increase in anterior chamber (AC) cell grade or vitreous haze (VH) grade or a decrease in best corrected visual acuity (BCVA).

Study UV I evaluated 217 subjects with active uveitis while being treated with corticosteroids (oral prednisone at a dose of 10 to 60 mg/day). All subjects received a standardized dose of prednisone 60 mg/day at study entry followed by a mandatory taper schedule, with complete corticosteroid discontinuation by Week 15.

Study UV II evaluated 226 subjects with inactive uveitis while being treated with corticosteroids (oral prednisone 10 to 35 mg/day) at baseline to control their disease. Subjects subsequently underwent a mandatory taper schedule, with complete corticosteroid discontinuation by Week 19.

Clinical Response

Results from both studies demonstrated statistically significant reduction of the risk of treatment failure in subjects treated with adalimumab versus subjects receiving placebo. In both studies, all components of the primary endpoint contributed cumulatively to the overall difference between adalimumab and placebo groups (Table 20).

Table 20. Time to Treatment Failure in Studies UV I and UV II
 | UV I |  |  | UV II
 | Placebo (N = 107) | Adalimumab (N = 110) | HR [95% CI]a | Placebo (N = 111) | Adalimumab (N = 115) | HR [95% CI]a
Failureb n (%) | 84 (78.5) | 60 (54.5) | 0.50 [0.36, 0.70] | 61 (55.0) | 45 (39.1) | 0.57 [0.39, 0.84]
Median Time to Failure (Months) [95% CI] | 3.0 [2.7, 3.7] | 5.6 [3.9, 9.2] | N/A | 8.3 [4.8, 12.0] | NEc | N/A
a HR of adalimumab versus placebo from proportional hazards regression with treatment as factor.
b Treatment failure at or after Week 6 in Study UV I, or at or after Week 2 in Study UV II, was counted as event. Subjects who discontinued the study were censored at the time of dropping out.
cNE = not estimable. Fewer than half of at-risk subjects had an event.

Figure 3: Kaplan-Meier Curves Summarizing Time to Treatment Failure on or after Week 6 (Study UV I) or Week 2 (Study UV II)

Note: P# = Placebo (Number of Events/Number at Risk); A# = Adalimumab (Number of Events/Number at Risk).

15 REFERENCES

1. National Cancer Institute. Surveillance, Epidemiology, and End Results Database (SEER) Program. SEER Incidence Crude Rates, 17 Registries, 2000-2007

16 HOW SUPPLIED/STORAGE AND HANDLING

Adalimumab-bwwd is supplied as a preservative-free, sterile, clear to opalescent, and colorless to pale brown solution for subcutaneous administration. The following packaging configurations are available.

- Adalimumab-bwwd Autoinjector Carton - 40 mg/0.8 mL
  Adalimumab-bwwd is supplied in a carton containing two single-dose autoinjectors. Each single-dose autoinjector contains a 1 mL prefilled glass syringe with a fixed ½ inch needle, providing 40 mg/0.8 mL of Adalimumab-bwwd. The NDC number is 83457-184-01.
- Adalimumab-bwwd Prefilled Syringe Carton - 40 mg/0.8 mL
  Adalimumab-bwwd is supplied in a carton containing two single-dose, 1 mL prefilled glass syringes, each with a fixed ½ inch needle, providing 40 mg/0.8 mL of Adalimumab-bwwd. The NDC number is 83457-183-01.
- Single-dose Institutional Use Vial Carton - 40 mg/0.8 mL
  Adalimumab-bwwd is supplied for institutional use only in a carton containing a single-dose, glass vial providing 40 mg/0.8 mL of Adalimumab-bwwd. The NDC number is 83457-185-01.
- Adalimumab-bwwd Autoinjector Carton - 40 mg/0.4 mL
  Adalimumab-bwwd is supplied in a carton containing two single-dose autoinjectors. Each single-dose autoinjector contains a 1 mL prefilled glass syringe with a fixed ½ inch needle, providing 40 mg/0.4 mL of Adalimumab-bwwd. The NDC number is 83457-187-01.
- Adalimumab-bwwd Prefilled Syringe Carton - 40 mg/0.4 mL
  Adalimumab-bwwd is supplied in a carton containing two single-dose, 1 mL prefilled glass syringes each with a fixed ½ inch needle, providing 40 mg/0.4 mL of Adalimumab-bwwd. The NDC number is 83457-186-01.

Storage and Stability

Do not use beyond the expiration date on the container. Adalimumab-bwwd must be refrigerated at 36°F to 46°F (2°C to 8°C). DO NOT FREEZE. Do not use if frozen even if it has been thawed.

Store in original carton until time of administration to protect from light.

If needed, for example when traveling, Adalimumab-bwwd autoinjector or prefilled syringe may be stored at room temperature up to a maximum of 77°F (25°C) for a period of up to 14 days, with protection from light. Adalimumab-bwwd autoinjector or prefilled syringe should be discarded if not used within the 14-day period. Record the date when Adalimumab-bwwd autoinjector or prefilled syringe is first removed from the refrigerator in the spaces provided on the autoinjector or prefilled syringe carton.

Do not store Adalimumab-bwwd in extreme heat or cold.

17 PATIENT COUNSELING INFORMATION

Advise the patient or caregiver to read the FDA-approved patient labeling (Medication Guide and Instructions for Use).

Infections

Inform patients that Adalimumab-bwwd may lower the ability of their immune system to fight infections. Instruct patients of the importance of contacting their doctor if they develop any symptoms of infection, including tuberculosis, invasive fungal infections, and reactivation of hepatitis B virus infections [see Warnings and Precautions (5.1, 5.2, 5.4)].

Malignancies

Counsel patients about the risk of malignancies while receiving Adalimumab-bwwd [see Warnings and Precautions (5.2)].

Hypersensitivity Reactions

Advise patients to seek immediate medical attention if they experience any symptoms of severe hypersensitivity reactions [see Warnings and Precautions (5.3)].

Other Medical Conditions

Advise patients to report any signs of new or worsening medical conditions such as congestive heart failure, neurological disease, autoimmune disorders, or cytopenias. Advise patients to report any symptoms suggestive of a cytopenia such as bruising, bleeding, or persistent fever [see Warnings and Precautions (5.5, 5.6, 5.8, 5.9)].

Instructions on Injection Technique

Inform patients that the first injection is to be performed under the supervision of a qualified health care professional. If a patient or caregiver is to administer Adalimumab-bwwd, instruct them in injection techniques and assess their ability to inject subcutaneously to ensure the proper administration of Adalimumab-bwwd [see Instructions for Use].

For patients who will use the Adalimumab-bwwd autoinjector, tell them that they:

- May hear a 1st click when they place the green base straight on their skin and push the entire device down firmly. The click means the start of the injection.
- Must keep holding the Adalimumab-bwwd autoinjector against their skin until all of the medicine is injected.
- Will know that the injection has finished when the yellow indicator fills the medication window and stops moving. Also they may hear a 2nd click several seconds after starting the injection.

Instruct patients to dispose of their used needles and syringes or used autoinjector in a FDA-cleared sharps disposal container immediately after use. Instruct patients not to dispose of loose needles and syringes or autoinjector in their household trash. Instruct patients that if they do not have a FDA-cleared sharps disposal container, they may use a household container that is made of a heavy-duty plastic, can be closed with a tight-fitting and puncture-resistant lid without sharps being able to come out, upright and stable during use, leak-resistant, and properly labeled to warn of hazardous waste inside the container.

Instruct patients that when their sharps disposal container is almost full, they will need to follow their community guidelines for the correct way to dispose of their sharps disposal container. Instruct patients that there may be state or local laws regarding disposal of used needles and syringes. Refer patients to the FDA’s website at http://www.fda.gov/safesharpsdisposal for more information about safe sharps disposal, and for specific information about sharps disposal in the state that they live in.

Instruct patients not to dispose of their used sharps disposal container in their household trash unless their community guidelines permit this. Instruct patients not to recycle their used sharps disposal container.

Manufactured by: Samsung Bioepis Co., Ltd., 76, Songdogyoyuk-ro, Yeonsu-gu, Incheon, 21987, Republic of Korea
U.S. License No. 2046

Manufactured for:

Cordavis Limited
Dublin, Ireland

Medication Guide

Adalimumab-bwwd (ada-LIM-u-mab bwwd)

injection, for subcutaneous use

Read the Medication Guide that comes with Adalimumab-bwwd before you start taking it and each time you get a refill. There may be new information. This Medication Guide does not take the place of talking with your doctor about your medical condition or treatment.

What is the most important information I should know about Adalimumab-bwwd?

Adalimumab-bwwd is a medicine that affects your immune system. Adalimumab-bwwd can lower the ability of your immune system to fight infections. Serious infections have happened in people taking adalimumab products. These serious infections include tuberculosis (TB) and infections caused by viruses, fungi or bacteria that have spread throughout the body. Some people have died from these infections.

- Your doctor should test you for TB before starting Adalimumab-bwwd.
- Your doctor should check you closely for signs and symptoms of TB during treatment with Adalimumab-bwwd.

You should not start taking Adalimumab-bwwd if you have any kind of infection unless your doctor says it is okay.

Before starting Adalimumab-bwwd, tell your doctor if you:

- think you have an infection or have symptoms of an infection such as:

◦ fever, sweats, or chills

◦ warm, red, or painful skin or sores on your body

◦ muscle aches

◦ diarrhea or stomach pain

◦ cough

◦ burning when you urinate or urinate more often than normal

◦ shortness of breath

◦ feel very tired

◦ blood in phlegm

◦ weight loss

- are being treated for an infection.
- get a lot of infections or have infections that keep coming back.
- have diabetes.
- have TB, or have been in close contact with someone with TB.
- were born in, lived in, or traveled to countries where there is more risk for getting TB. Ask your doctor if you are not sure.
- live or have lived in certain parts of the country (such as the Ohio and Mississippi River valleys) where there is an increased risk for getting certain kinds of fungal infections (histoplasmosis, coccidioidomycosis, or blastomycosis). These infections may happen or become more severe if you use Adalimumab-bwwd. Ask your doctor if you do not know if you have lived in an area where these infections are common.
- have or have had hepatitis B.
- use the medicine ORENCIA (abatacept), KINERET (anakinra), RITUXAN (rituximab), IMURAN (azathioprine), or PURINETHOL (6–mercaptopurine, 6-MP).
- are scheduled to have major surgery.

After starting Adalimumab-bwwd, call your doctor right away if you have an infection, or any sign of an infection.

Adalimumab-bwwd can make you more likely to get infections or make any infection that you may have worse.

Cancer

- For children and adults taking Tumor Necrosis Factor (TNF)-blockers, including Adalimumab-bwwd, the chances of getting cancer may increase.
- There have been cases of unusual cancers in children, teenagers, and young adults using TNF-blockers.
- People with rheumatoid arthritis (RA), especially more serious RA, may have a higher chance for getting a kind of cancer called lymphoma.
- If you use TNF blockers including Adalimumab-bwwd, your chance of getting two types of skin cancer may increase (basal cell cancer and squamous cell cancer of the skin). These types of cancer are generally not life-threatening if treated. Tell your doctor if you have a bump or open sore that does not heal.
- Some people receiving TNF blockers including Adalimumab-bwwd developed a rare type of cancer called hepatosplenic T-cell lymphoma. This type of cancer often results in death. Most of these people were male teenagers or young men. Also, most people were being treated for Crohn’s disease or ulcerative colitis with another medicine called IMURAN® (azathioprine) or PURINETHOL® (6-mercaptopurine, 6–MP).

What is Adalimumab-bwwd?

Adalimumab-bwwd is a medicine called a Tumor Necrosis Factor (TNF) blocker. Adalimumab-bwwd is used:

- to reduce the signs and symptoms of:
  - moderate to severe rheumatoid arthritis (RA) in adults. Adalimumab-bwwd can be used alone, with methotrexate, or with certain other medicines.
  - moderate to severe polyarticular juvenile idiopathic arthritis (JIA) in children 2 years and older. Adalimumab-bwwd can be used alone, or with methotrexate.
  - psoriatic arthritis (PsA) in adults. Adalimumab-bwwd can be used alone or with certain other medicines.
  - ankylosing spondylitis (AS) in adults.
  - moderate to severe hidradenitis suppurativa (HS) in adults.
- to treat moderate to severe Crohn’s disease (CD) in adults and children 6 years of age and older.
- to treat moderate to severe ulcerative colitis (UC) in adults. It is not known if adalimumab products are effective in people who stopped responding to or could not tolerate TNF-blocker medicines.
- to treat moderate to severe chronic (lasting a long time) plaque psoriasis (Ps) in adults who have the condition in many areas of their body and who may benefit from taking injections or pills (systemic therapy) or phototherapy (treatment using ultraviolet light alone or with pills).
- to treat non-infectious intermediate, posterior, and panuveitis in adults

What should I tell my doctor before taking Adalimumab-bwwd?

Adalimumab-bwwd may not be right for you. Before starting Adalimumab-bwwd, tell your doctor about all of your medical conditions, including if you:

- have an infection. See “What is the most important information I should know about Adalimumab-bwwd?”
- have or have had cancer.
- have any numbness or tingling or have a disease that affects your nervous system such as multiple sclerosis or Guillain-Barré syndrome.
- have or had heart failure.
- have recently received or are scheduled to receive a vaccine. You may receive vaccines, except for live vaccines while using Adalimumab-bwwd. Children should be brought up to date with all vaccines before starting Adalimumab-bwwd.
- are allergic to Adalimumab-bwwd or to any of its ingredients. See the end of this Medication Guide for a list of ingredients in Adalimumab-bwwd.
- are pregnant or plan to become pregnant, breastfeeding or plan to breastfeed. You and your doctor should decide if you should take Adalimumab-bwwd while you are pregnant or breastfeeding.
- have a baby and you were using Adalimumab-bwwd during your pregnancy. Tell your baby’s doctor before your baby receives any vaccines.

Tell your doctor about all the medicines you take, including prescription and over-the-counter medicines, vitamins, and herbal supplements.

Especially tell your doctor if you use:

- ORENCIA (abatacept), KINERET (anakinra), REMICADE (infliximab), ENBREL (etanercept), CIMZIA (certolizumab pegol) or SIMPONI (golimumab), because you should not use Adalimumab-bwwd while you are also using one of these medicines.
- RITUXAN (rituximab). Your doctor may not want to give you Adalimumab-bwwd if you have received RITUXAN (rituximab) recently.
- IMURAN (azathioprine) or PURINETHOL (6–mercaptopurine, 6-MP).

Keep a list of your medicines with you to show your doctor and pharmacist each time you get a new medicine.

How should I take Adalimumab-bwwd?

- Adalimumab-bwwd is given by an injection under the skin. Your doctor will tell you how often to take an injection of Adalimumab-bwwd. This is based on your condition to be treated. Do not inject Adalimumab-bwwd more often than you were prescribed.
- See the Instructions for Use inside the carton for complete instructions for the right way to prepare and inject Adalimumab-bwwd.
- Make sure you have been shown how to inject Adalimumab-bwwd before you do it yourself. You can call your doctor or 1-833-267-3070 if you have any questions about giving yourself an injection. Someone you know can also help you with your injection after they have been shown how to prepare and inject Adalimumab-bwwd.
- Do not try to inject Adalimumab-bwwd yourself until you have been shown the right way to give the injections. If your doctor decides that you or a caregiver may be able to give your injections of Adalimumab-bwwd at home, you should receive training on the right way to prepare and inject Adalimumab-bwwd.
- Do not miss any doses of Adalimumab-bwwd unless your doctor says it is okay. If you forget to take Adalimumab-bwwd, inject a dose as soon as you remember. Then, take your next dose at your regular scheduled time. This will put you back on schedule. In case you are not sure when to inject Adalimumab-bwwd, call your doctor or pharmacist.
- If you take more Adalimumab-bwwd than you were told to take, call your doctor.

What are the possible side effects of Adalimumab-bwwd?

Adalimumab-bwwd can cause serious side effects, including:

See “What is the most important information I should know about Adalimumab-bwwd?”

- Serious Infections.
  Your doctor will examine you for TB and perform a test to see if you have TB. If your doctor feels that you are at risk for TB, you may be treated with medicine for TB before you begin treatment with Adalimumab-bwwd and during treatment with Adalimumab-bwwd. Even if your TB test is negative your doctor should carefully monitor you for TB infections while you are taking Adalimumab-bwwd. People who had a negative TB skin test before receiving adalimumab products have developed active TB. Tell your doctor if you have any of the following symptoms while taking or after taking Adalimumab-bwwd:

◦ cough that does not go away

◦ weight loss

◦ low grade fever

◦ loss of body fat and muscle (wasting)

- Hepatitis B infection in people who carry the virus in their blood.
  If you are a carrier of the hepatitis B virus (a virus that affects the liver), the virus can become active while you use Adalimumab-bwwd. Your doctor should do blood tests before you start treatment, while you are using Adalimumab-bwwd, and for several months after you stop treatment with Adalimumab-bwwd. Tell your doctor if you have any of the following symptoms of a possible hepatitis B infection:

◦ muscle aches

◦ clay-colored bowel movements

◦ feel very tired

◦ fever

◦ dark urine

◦ chills

◦ skin or eyes look yellow

◦ stomach discomfort

◦ little or no appetite

◦ skin rash

◦ vomiting

- Allergic reactions. Allergic reactions can happen in people who use Adalimumab-bwwd. Call your doctor or get medical help right away if you have any of these symptoms of a serious allergic reaction:

◦ hives

◦ swelling of your face, eyes, lips or mouth

◦ trouble breathing

- Nervous system problems. Signs and symptoms of a nervous system problem include: numbness or tingling, problems with your vision, weakness in your arms or legs, and dizziness.
- Blood problems. Your body may not make enough of the blood cells that help fight infections or help to stop bleeding. Symptoms include a fever that does not go away, bruising or bleeding very easily, or looking very pale.
- New heart failure or worsening of heart failure you already have. Call your doctor right away if you get new worsening symptoms of heart failure while taking Adalimumab-bwwd, including:

◦ shortness of breath

◦ swelling of your ankles or feet

◦ sudden weight gain

- Immune reactions including a lupus-like syndrome. Symptoms include chest discomfort or pain that does not go away, shortness of breath, joint pain, or a rash on your cheeks or arms that gets worse in the sun. Symptoms may improve when you stop Adalimumab-bwwd.
- Liver problems. Liver problems can happen in people who use TNF-blocker medicines. These problems can lead to liver failure and death. Call your doctor right away if you have any of these symptoms:

◦ feel very tired

◦ skin or eyes look yellow

◦ poor appetite or vomiting

◦ pain on the right side of your stomach (abdomen)

- Psoriasis. Some people using adalimumab products had new psoriasis or worsening of psoriasis they already had. Tell your doctor if you develop red scaly patches or raised bumps that are filled with pus. Your doctor may decide to stop your treatment with Adalimumab-bwwd.

Call your doctor or get medical care right away if you develop any of the above symptoms. Your treatment with Adalimumab-bwwd may be stopped.

The most common side effects of Adalimumab-bwwd include:

- injection site reactions: redness, rash, swelling, itching, or bruising. These symptoms usually will go away within a few days. Call your doctor right away if you have pain, redness or swelling around the injection site that does not go away within a few days or gets worse.
- upper respiratory infections (including sinus infections)
- headaches
- rash

These are not all the possible side effects with Adalimumab-bwwd. Tell your doctor if you have any side effect that bothers you or that does not go away. Ask your doctor or pharmacist for more information.

Call your doctor for medical advice about side effects. You may report side effects to the FDA at 1-800-FDA-1088.

How should I store Adalimumab-bwwd?

- Store Adalimumab-bwwd in the refrigerator at 36ºF to 46ºF (2ºC to 8ºC). Store Adalimumab-bwwd in the original carton until use to protect it from light.
- Do not freeze Adalimumab-bwwd. Do not use Adalimumab-bwwd if frozen, even if it has been thawed.
- Refrigerated Adalimumab-bwwd may be used until the expiration date printed on the Adalimumab-bwwd carton, autoinjector or prefilled syringe. Do not use Adalimumab-bwwd after the expiration date.
- If needed, for example when you are traveling, you may also store Adalimumab-bwwd autoinjector or prefilled syringe at room temperature up to 77°F (25°C) for up to 14 days. Store Adalimumab-bwwd autoinjector or prefilled syringe in the original carton until use to protect it from light.
- Throw away Adalimumab-bwwd autoinjector or prefilled syringe if it has been kept at room temperature and not been used within 14 days.
- Record the date you first remove Adalimumab-bwwd autoinjector or prefilled syringe from the refrigerator in the spaces provided on the carton.
- Do not store Adalimumab-bwwd in extreme heat or cold.
- The solution should be clear and colorless to pale brown. Do not use an autoinjector or prefilled syringe if the liquid is cloudy, discolored, or has flakes or particles in it.
- Do not drop or crush Adalimumab-bwwd. The prefilled syringe is glass.

Keep Adalimumab-bwwd, injection supplies, and all other medicines out of the reach of children.

General information about the safe and effective use of Adalimumab-bwwd

Medicines are sometimes prescribed for purposes other than those listed in a Medication Guide. Do not use Adalimumab-bwwd for a condition for which it was not prescribed. Do not give Adalimumab-bwwd to other people, even if they have the same condition. It may harm them.

This Medication Guide summarizes the most important information about Adalimumab-bwwd. If you would like more information, talk with your doctor. You can ask your doctor or pharmacist for information about Adalimumab-bwwd that is written for health professionals. For more information call Cordavis Limited at 1-833-267-3070.

What are the ingredients in Adalimumab-bwwd?

Active ingredient: adalimumab-bwwd

Adalimumab-bwwd autoinjector 40 mg/0.8 mL, Adalimumab-bwwd 40 mg/0.8 mL prefilled syringe, and Adalimumab-bwwd 40 mg/0.8 mL institutional use vial:

Inactive ingredients: citric acid monohydrate, L-histidine, L-histidine hydrochloride monohydrate, polysorbate 20, sodium citrate dihydrate, sorbitol, and Water for Injection, USP.

Adalimumab-bwwd autoinjector 40 mg/0.4 mL and Adalimumab-bwwd 40 mg/0.4 mL prefilled syringe:
Inactive ingredients: L-histidine, L-histidine hydrochloride monohydrate, mannitol, polysorbate 20, sodium phosphate dibasic heptahydrate, sodium phosphate monobasic monohydrate, sodium succinate dibasic, succinic acid, and Water for Injection, USP

Manufactured by: Samsung Bioepis Co., Ltd., 76, Songdogyoyuk-ro, Yeonsu-gu, Incheon, 21987, Republic of Korea

U.S. License No. 2046
Manufactured for: Cordavis Limited, Dublin, Ireland

This Medication Guide has been approved by the U.S. Food and Drug Administration.

Revised: 10/2025

INSTRUCTIONS FOR USE

Adalimumab-bwwd (ada-LIM-u-mab bwwd)
40 mg/0.8 mL
Single Dose Prefilled Syringe

For subcutaneous (under the skin) use only

Do not try to inject Adalimumab-bwwd yourself until you have been shown the right way to give an injection and have read and understand this Instructions for Use. If your doctor decides that you or a caregiver may be able to give your injection of Adalimumab-bwwd at home, you should receive training on the right way to prepare and inject Adalimumab-bwwd. It is important that you read, understand, and follow these instructions so that you inject Adalimumab-bwwd the right way. Call your healthcare provider if you or your caregiver have any questions about the right way to inject Adalimumab-bwwd.

To help you remember when to inject Adalimumab-bwwd, you can mark your calendar ahead of time.

The following instructions are for preparing and giving 1 dose of Adalimumab-bwwd using a single dose prefilled syringe. Read this Instructions for Use before you start using Adalimumab-bwwd.

What is included in this Instructions for Use

- Your single dose prefilled syringe
- Caring for your syringe
- How to inject with your syringe
- Extra tips for injecting Adalimumab-bwwd
- Frequently asked questions (FAQs)

Your single dose prefilled syringe:

After you push the plunger all the way down, the needle will be covered automatically (retract) to help prevent needle stick injury.

Caring for your syringe

How should I store Adalimumab-bwwd?

Store Adalimumab-bwwd in the refrigerator between 36°F to 46°F (2°C to 8°C).

- Do not freeze Adalimumab-bwwd. Do not use Adalimumab-bwwd if frozen, even if it has been thawed.
- Refrigerated Adalimumab-bwwd may be used until the expiration date printed on the Adalimumab-bwwd carton or prefilled syringe. Do not use Adalimumab-bwwd after the expiration date.
- If needed, for example when you are traveling, you may also store Adalimumab-bwwd at room temperature up to 77°F (25°C) for up to 14 days. Throw away Adalimumab-bwwd if it has been kept at room temperature and not been used within 14 days.

Store Adalimumab-bwwd in the original carton until you use it to protect it from sunlight and indoor light.

- Record the date you first remove Adalimumab-bwwd from the refrigerator in the spaces provided on the carton.
- Do not store Adalimumab-bwwd in extreme heat or cold.
- Do not drop or crush Adalimumab-bwwd. The prefilled syringe is glass.

Keep Adalimumab-bwwd, injection supplies, and all other medicines out of the reach of children.

Use each syringe only 1 time. Do not reuse a syringe.

Throw away your used syringe in a sharps container.

If you have any questions, call the hotline at 1-833-267-3070.

How to inject with your syringe

Step 1: Remove your prefilled syringe from the refrigerator and wait 15 to 30 minutes

- For a more comfortable injection, you should wait 15 to 30 minutes for the medicine in your prefilled syringe to reach room temperature (see Figure B).
- Do not warm Adalimumab-bwwd in any other way (for example, do not warm it in a microwave or in hot water).

Step 2: Gather supplies

- You will need the following supplies for each injection of Adalimumab-bwwd (see Figure C).
  Find a clean, flat surface to place the supplies on.
  - 1 Adalimumab-bwwd prefilled syringe
  - 1 alcohol swab (not included in your Adalimumab-bwwd carton)
  - cotton ball or gauze (not included in your Adalimumab-bwwd carton)
  - puncture-resistant sharps disposal container for Adalimumab-bwwd prefilled syringe disposal (not included in your Adalimumab-bwwd carton). See “How should I throw away (dispose of) the used prefilled syringes?” section at the end of this Instructions for Use.

If you do not have all the supplies you need to give yourself an injection, go to a pharmacy or call your pharmacist.

Step 3: Inspect the medicine and check the expiration date

- You should always check the expiration date to make sure Adalimumab-bwwd prefilled syringe has not expired. Do not use if the expiration date has passed.
- Do not use Adalimumab-bwwd if:
  - the prefilled syringe is frozen or has been left in sunlight and indoor light.
  - it has been kept at room temperature for longer than 14 days or Adalimumab-bwwd has been stored above 77ºF (25ºC).
  - See the “Caring for your syringe” and “Frequently asked questions (FAQs)” sections of this Instructions for Use.
- The solution should be clear and colorless to pale brown. Do not use the prefilled syringe if the liquid is cloudy, discolored, or has flakes or particles in it (see Figure D).
- You may see one or more air bubbles in the body with window, and that is okay. There is no reason to remove it.
- Do not remove the needle cap until Step 5.

Step 4: Choose the injection site and clean the skin

- Wash and dry your hands.
- Choose an injection site on your body. The recommended injection site is the front of the thigh or lower abdomen (belly), but not the area 2 inches (5 cm) around your belly button (naval) (see Figure E).
- Choose a different site each time you give yourself an injection.
- Do not inject into areas where the skin is tender, bruised, red, scaly or hard. Avoid areas with scars or stretch marks. If you have psoriasis, you should not inject directly into areas with psoriasis plaques.
- Wipe your skin at the injection site with an alcohol swab in a circular motion. Let the skin dry before injecting.
- Do not touch this area again before giving the injection.

Step 5: Pull off the needle cap

- Carefully pull off the needle cap straight off to remove it from the prefilled syringe (see Figure F).
- Throw away the needle cap.
- Do not touch the needle with your fingers or let the needle touch anything.

Step 6: Pinch the skin and insert the needle

- Gently pinch your skin at the injection site and insert the needle all the way into your skin at about a 45 degree angle (see Figure G).

Step 7: Push the plunger all the way

- Hold the syringe and press the plunger all the way down until the syringe is empty (see Figure H).
- Then take your thumb off the plunger to let the needle retract into the body of the syringe.

Step 8: Remove the syringe

- Pull the syringe away from your skin at the same angle that you pushed it in.
- Make sure that the needle has retracted (see Figure I).
- Not sure if you received your dose? Call 1-833-267-3070.

Step 9: How should I throw away (dispose of) the used prefilled syringes?

- Put your used syringes in an FDA-cleared sharps disposal container right away after use. Do not throw away (dispose of) syringes in your household trash (see Figure I).
- If you do not have an FDA-cleared sharps disposal container, you may use a household container that is:
  - made of a heavy-duty plastic,
  - can be closed with a tight-fitting, puncture-resistant lid, without sharps being able to come out,
  - upright and stable during use,
  - leak-resistant, and
  - properly labeled to warn of hazardous waste inside the container.
- When your sharps disposal container is almost full, you will need to follow your community guidelines for the right way to dispose of sharps disposal containers. There may be state or local laws about how you should throw away used syringes. For more information about safe sharps disposal, and for specific information about sharps disposal in the state that you live in, go to the FDA’s website at: http://www.fda.gov/safesharpsdisposal.
- Do not dispose of your used sharps disposal container in your household trash unless your community guidelines permit this. Do not recycle your used sharps disposal container.

Extra tips for injecting Adalimumab-bwwd

Now that you understand the basics of giving yourself an injection, here are some extra tips to help you.

Choose a fatty area for injection

- Fatty areas, like your stomach, are generally the best injection sites. Fatty areas are easier to pinch and are good for inserting the needle correctly.

Use a different injection site every time

- When choosing an injection site, select an area that has not recently been used to avoid soreness and bruises.

Finalize your injection

- After the injection is complete, you can use a cotton ball or gauze to cover the injection site if there is a little bleeding.

Frequently asked questions (FAQs)

If you have questions, read through these FAQs to learn more. If you still have any questions, call 1-833-267-3070.

What should I do if:

My syringe is out of the refrigerator for more than 30 minutes

- It is okay to leave your syringe out for up to 14 days before injecting, as long as it is kept away from sunlight and indoor light. If your syringe has been at room temperature for more than 14 days, call 1-833-267-3070.

The medicine in my syringe is not clear, colorless to pale brown, free of particles, or is expired

- If the medicine in your syringe is not clear, colorless to pale brown, or free of particles, do not use it. If it is expired, do not use it. Get a new syringe. Call 1-833-267-3070.

I see air bubbles in my syringe

- It is normal to see small air bubbles in your syringe. There is no reason to remove them.

I took off my needle cap before I was ready to inject

- Do not put the needle cap back on. This could bend or damage the needle. You might accidentally stick yourself or waste the medicine. Call 1-833-267-3070.

I dropped my syringe

- If you dropped your syringe with the cap on, it is okay to use the syringe.
  If you dropped your syringe with the cap off, do not use it. The needle might be dirty or damaged. Call 1-833-267-3070.

The syringe is damaged or broken

- Do not use a damaged syringe. Get a new syringe. Call 1-833-267-3070.

The needle never retracted

- If the needle never retracted into the body, the plunger was not pushed all the way down. Press the plunger harder to activate the shield. If you still have trouble, call 1-833-267-3070.

I am not sure I received my full dose

- You received your full dose if:
  - The plunger was pushed all the way down
  - The needle retracted into the shield
  - All of the medicine went into your skin and did not leak out. (If you see a drop, that is okay)
- If you are still not sure, call 1-833-267-3070.

This Instructions for Use has been approved by the U.S. Food and Drug Administration.

Manufactured by: Samsung Bioepis Co., Ltd., 76, Songdogyoyuk-ro, Yeonsu-gu, Incheon, 21987, Republic of Korea

U.S. License No. 2046

Manufactured for: Cordavis Limited, Dublin, Ireland

Last Revised <10/2025>

INSTRUCTIONS FOR USE

Adalimumab-bwwd (ada-LIM-u-mab bwwd)
40 mg/0.8 mL
Single Dose Autoinjector

For subcutaneous (under the skin) use only

Do not try to inject Adalimumab-bwwd yourself until you have been shown the right away to give an injection and have read and understand this Instructions for Use. If your doctor decides that you or a caregiver may be able to give your injections of Adalimumab-bwwd at home, you should receive training on the right way to prepare and inject Adalimumab-bwwd. It is important that you read, understand, and follow these instructions so that you inject Adalimumab-bwwd the right way. Call your healthcare provider if you or your caregiver have any questions about the right way to inject Adalimumab-bwwd.

To help you remember when to inject Adalimumab-bwwd, you can mark your calendar ahead of time.

The following instructions are for preparing and giving 1 dose of Adalimumab-bwwd autoinjector. Read this Instructions for Use before you start using Adalimumab-bwwd autoinjector.

What is included in this Instructions for Use

- Your Adalimumab-bwwd autoinjector
- Caring for your autoinjector
- How to inject with your autoinjector
- Extra tips for injecting Adalimumab-bwwd
- Frequently asked questions (FAQs)

Your Adalimumab-bwwd autoinjector:

The needle is hidden below the green base. When you push the Adalimumab-bwwd autoinjector onto your skin, the injection will start automatically.

Important: There is no button on your Adalimumab-bwwd autoinjector.

Caring for your autoinjector

How should I store Adalimumab-bwwd autoinjector?

Store Adalimumab-bwwd in the refrigerator between 36°F to 46°F (2°C to 8°C).

- Do not freeze Adalimumab-bwwd. Do not use Adalimumab-bwwd if frozen, even if it has been thawed.
- Refrigerated Adalimumab-bwwd may be used until the expiration date printed on the Adalimumab-bwwd carton or autoinjector. Do not use Adalimumab-bwwd after the expiration date.
- If needed, for example when you are traveling, you may also store Adalimumab-bwwd at room temperature up to 77°F (25°C) for up to 14 days. Throw away Adalimumab-bwwd if it has been kept at room temperature and not been used within 14 days.

Store Adalimumab-bwwd in the original carton until you use it to protect it from sunlight and indoor light.

- Record the date you first remove Adalimumab-bwwd from the refrigerator in the spaces provided on the carton.
- Do not store Adalimumab-bwwd in extreme heat or cold.
- Do not drop or crush Adalimumab-bwwd. The prefilled syringe is glass.

Keep Adalimumab-bwwd, injection supplies, and all other medicines out of the reach of children.

Use each Adalimumab-bwwd autoinjector only 1 time. Do not reuse Adalimumab-bwwd autoinjector.

Throw away your used Adalimumab-bwwd autoinjector in a sharps container.

If you have any questions, call the hotline at 1-833-267-3070.

How to inject with your autoinjector

Step 1: Remove your Adalimumab-bwwd autoinjector from the refrigerator and wait 15 to 30 minutes

- For a more comfortable injection, you should wait 15 to 30 minutes for the medicine in autoinjector to reach room temperature (see Figure B).
- Do not warm Adalimumab-bwwd in any other way (for example, do not warm it in a microwave or in hot water).

Step 2: Gather supplies

- You will need the following supplies for each injection of Adalimumab-bwwd (see Figure C).
  Find a clean, flat surface to place the supplies on.
  - 1 Adalimumab-bwwd autoinjector
  - 1 alcohol swab (not included in your Adalimumab-bwwd carton)
  - cotton ball or gauze (not included in your Adalimumab-bwwd carton)
  - puncture-resistant sharps disposal container for Adalimumab-bwwd autoinjector disposal (not included in your Adalimumab-bwwd carton). See “How should I throw away (dispose of) the used autoinjectors?” section at the end of this Instructions for Use.

If you do not have all the supplies you need to give yourself an injection, go to a pharmacy or call your pharmacist.

Step 3: Inspect the medicine and expiration date

- You should always check the expiration date to make sure your autoinjector has not expired. Do not use if the expiration date has passed.
- Do not use Adalimumab-bwwd if:
  - the autoinjector is frozen or has been left in sunlight and indoor light.
  - it has been kept at room temperature for longer than 14 days or Adalimumab-bwwd has been stored above 77ºF (25 ºC).
  - see the “Caring for your autoinjector” and “Frequently asked questions (FAQs)” sections of this Instructions for Use.
- The solution should be clear and colorless to pale brown. Do not use the autoinjector if the liquid is cloudy, discolored, or has flakes or particles in it (see Figure D).
- You may see one or more air bubbles in the medicine window, and that is okay. There is no reason to remove it.
- Do not remove the needle cap until Step 5.

Step 4: Choose the injection site and clean the skin

- Wash and dry your hands.
- Choose an injection site on your body. The recommended injection site is the front of the thigh or lower abdomen (belly), but not the area 2 inches (5 cm) around your belly button (naval) (see Figure E).
- Choose a different site each time you give yourself an injection.
- Do not inject into areas where the skin is tender, bruised, red, scaly or hard. Avoid areas with scars or stretch marks. If you have psoriasis, you should not inject directly into areas with psoriasis plaques.
- Wipe your skin at the injection site with an alcohol swab in a circular motion. Let the skin dry before injecting.
- Do not touch this area again before giving the injection.

Step 5: Pull off the clear needle cap

- Carefully pull off the clear needle cap with a metal center straight off to remove it from the autoinjector (see Figure F).
- Throw away the needle cap.

Step 6: Place the green base of the autoinjector on your skin, press down, and hold

- Place the green base straight on your skin and push the entire device down firmly to start the injection.
- When you push down, the injection will start (see Figure G).
- You may hear the first click which means the injection has started.

Step 7: Keep holding the autoinjector

- Keep holding the autoinjector against your skin until the yellow indicator fills the medicine window and the yellow indicator stops moving (see Figure H).
- After a few seconds you may hear a second click. This means the injection is complete.

Step 8: Make sure the entire dose is given

- If the medicine window is all yellow, this means your dose is complete (see Figure I).
- Remove the autoinjector away from your skin. The needle should be covered by the green base.
- Not sure if you received your dose? Call 1-833-267-3070.

Step 9: How should I throw away (dispose of) the used autoinjectors?

- Put your used autoinjectors in an FDA-cleared sharps disposal container right away after use. Do not throw away (dispose of) autoinjectors in your household trash. (see Figure I)
- If you do not have an FDA-cleared sharps disposal container, you may use a household container that is:
  - made of a heavy-duty plastic,
  - can be closed with a tight-fitting, puncture-resistant lid, without sharps being able to come out,
  - upright and stable during use,
  - leak-resistant, and
  - properly labeled to warn of hazardous waste inside the container.
- When your sharps disposal container is almost full, you will need to follow your community guidelines for the right way to dispose of sharps disposal containers. There may be state or local laws about how you should throw away used autoinjectors. For more information about safe sharps disposal, and for specific information about sharps disposal in the state that you live in, go to the FDA’s website at: http://www.fda.gov/safesharpsdisposal.
- Do not dispose of your used sharps disposal container in your household trash unless your community guidelines permit this. Do not recycle your used sharps disposal container.

Extra tips for injecting Adalimumab-bwwd

Now that you understand the basics of giving yourself an injection, here are some extra tips to help you.

Use a different injection site every time

- When choosing an injection site, select an area that has not recently been used to avoid soreness and bruises.

Finalize your injection

- After the injection is complete, you can use a cotton ball or gauze to cover the injection site if there is a little bleeding.

Frequently asked questions (FAQs)

If you have questions, read through these FAQs to learn more. If you still have any questions, call 1-833-267-3070.

What should I do if:

My autoinjector is out of the refrigerator for more than 30 minutes

- It is okay to leave your autoinjector out for up to 14 days before injecting, as long as it is kept away from sunlight and indoor light. If your Adalimumab-bwwd autoinjector has been at room temperature for more than 14 days, call 1-833-267-3070.

The medicine in my Adalimumab-bwwd autoinjector is not clear, colorless to pale brown, free of particles, or is expired

- If your medicine in your Adalimumab-bwwd autoinjector is not clear, colorless to pale brown, or free of particles, do not use it. If it is expired, do not use it. Get a new autoinjector. Call 1-833-267-3070.

I see air bubbles in my autoinjector

- It is normal to see small air bubbles in your autoinjector. There is no reason to remove them.

I took off my autoinjector cap before I was ready to inject

- Do not put the autoinjector cap back on. This could bend or damage the needle. You might accidentally stick yourself or waste the medicine. Call 1-833-267-3070.

I dropped my autoinjector

- If you dropped your autoinjector with the cap on, it is okay to use the autoinjector.
  If you dropped your autoinjector with the cap off, do not use it. The needle might be dirty or damaged. Call 1-833-267-3070.

The autoinjector is damaged or broken

- Do not use a damaged autoinjector. Get a new autoinjector. Call 1-833-267-3070.

The entire medicine window is not yellow after injection

- If your medicine window is not entirely yellow after injection, you may not have received your full dose. Call 1-833-267-3070.

I am not sure I received my full dose

- You received your full dose if:
  - The entire medicine window is yellow at the end of injection
  - All of the medicine went into your skin and did not leak out. (If you see a drop, that is okay)
- If you are still not sure, call 1-833-267-3070.

This Instructions for Use has been approved by the U.S. Food and Drug Administration.

Manufactured by: Samsung Bioepis Co., Ltd., 76, Songdogyoyuk-ro, Yeonsu-gu, Incheon, 21987, Republic of Korea

U.S. License No. 2046

Manufactured for: Cordavis Limited, Dublin, Ireland

Last Revised <10/2025>

INSTRUCTIONS FOR USE

Adalimumab-bwwd (ada-LIM-u-mab bwwd)
40 mg/0.4 mL
Single Dose Prefilled Syringe

For subcutaneous (under the skin) use only

Do not try to inject Adalimumab-bwwd yourself until you have been shown the right way to give an injection and have read and understand this Instructions for Use. If your doctor decides that you or a caregiver may be able to give your injection of Adalimumab-bwwd at home, you should receive training on the right way to prepare and inject Adalimumab-bwwd. It is important that you read, understand, and follow these instructions so that you inject Adalimumab-bwwd the right way. Call your healthcare provider if you or your caregiver have any questions about the right way to inject Adalimumab-bwwd.

To help you remember when to inject Adalimumab-bwwd, you can mark your calendar ahead of time.

The following instructions are for preparing and giving 1 dose of Adalimumab-bwwd using a single dose prefilled syringe. Read this Instructions for Use before you start using Adalimumab-bwwd.

What is included in this Instructions for Use

- Your single dose prefilled syringe
- Caring for your syringe
- How to inject with your syringe
- How should I throw away (dispose of) the used prefilled syringes?
- Extra tips for injecting Adalimumab-bwwd
- Frequently asked questions (FAQs)

Your single dose prefilled syringe:

After you push the plunger all the way down, the needle will be covered automatically (retract) to help prevent needle stick injury.

Caring for your syringe

How should I store Adalimumab-bwwd?

Store Adalimumab-bwwd in the refrigerator between 36°F to 46°F (2°C to 8°C).

- Do not freeze Adalimumab-bwwd. Do not use Adalimumab-bwwd if frozen, even if it has been thawed.
- Refrigerated Adalimumab-bwwd may be used until the expiration date printed on the Adalimumab-bwwd carton or prefilled syringe. Do not use Adalimumab-bwwd after the expiration date.
- If needed, for example when you are traveling, you may also store Adalimumab-bwwd at room temperature up to 77°F (25°C) for up to 14 days. Throw away Adalimumab-bwwd if it has been kept at room temperature and not been used within 14 days.

Store Adalimumab-bwwd in the original carton until you use it to protect it from sunlight and indoor light.

- Record the date you first remove Adalimumab-bwwd from the refrigerator in the spaces provided on the carton.
- Do not store Adalimumab-bwwd in extreme heat or cold.
- Do not drop or crush Adalimumab-bwwd. The prefilled syringe is glass.

Keep Adalimumab-bwwd, injection supplies, and all other medicines out of the reach of children.

Use each syringe only 1 time. Do not reuse a syringe.

Throw away your used syringe in a sharps container.

If you have any questions, call the hotline at 1-833-267-3070.

How to inject with your syringe

Step 1: Remove your prefilled syringe from the refrigerator and wait 15 to 30 minutes

- For a more comfortable injection, you should wait 15 to 30 minutes for the medicine in your prefilled syringe to reach room temperature (see Figure B).
- Do not warm Adalimumab-bwwd in any other way (for example, do not warm it in a microwave or in hot water).

Step 2: Gather supplies

- You will need the following supplies for each injection of Adalimumab-bwwd (see Figure C).
  Find a clean, flat surface to place the supplies on.
  - 1 Adalimumab-bwwd prefilled syringe
  - 1 alcohol swab (not included in your Adalimumab-bwwd carton)
  - cotton ball or gauze (not included in your Adalimumab-bwwd carton)
  - puncture-resistant sharps disposal container for Adalimumab-bwwd prefilled syringe disposal (not included in your Adalimumab-bwwd carton). See “How should I throw away (dispose of) the used prefilled syringes?” section at the end of this Instructions for Use.

If you do not have all the supplies you need to give yourself an injection, go to a pharmacy or call your pharmacist.

Step 3: Inspect the medicine and check the expiration date

- You should always check the expiration date to make sure Adalimumab-bwwd prefilled syringe has not expired. Do not use if the expiration date has passed.
- Do not use Adalimumab-bwwd if:
  - the prefilled syringe is frozen or has been left in sunlight and indoor light.
  - it has been kept at room temperature for longer than 14 days or Adalimumab-bwwd has been stored above 77°F (25°C).
  - See the “Caring for your syringe” and “Frequently asked questions (FAQs)” sections of this Instructions for Use.
- The solution should be clear and colorless to pale brown. Do not use the prefilled syringe if the liquid is cloudy, discolored, or has flakes or particles in it (see Figure D).
- You may see one or more air bubbles in the body with window, and that is okay. There is no reason to remove it.
- Do not remove the needle cap until Step 5.

Step 4: Choose the injection site and clean the skin

- Wash and dry your hands.
- Choose an injection site on your body. The recommended injection site is the front of the thigh or lower abdomen (belly), but not the area 2 inches (5 cm) around your belly button (naval) (see Figure E).
- Choose a different site each time you give yourself an injection.
- Do not inject into areas where the skin is tender, bruised, red, scaly or hard. Avoid areas with scars or stretch marks. If you have psoriasis, you should not inject directly into areas with psoriasis plaques.
- Wipe your skin at the injection site with an alcohol swab in a circular motion. Let the skin dry before injecting.
- Do not touch this area again before giving the injection.

Step 5: Pull off the needle cap

- Carefully pull off the needle cap straight off to remove it from the prefilled syringe (see Figure F).
- Throw away the needle cap.
- Do not touch the needle with your fingers or let the needle touch anything.

Step 6: Pinch the skin and insert the needle

- Gently pinch your skin at the injection site and insert the needle all the way into your skin at about a 45 degree angle (see Figure G).

Step 7: Push the plunger all the way

- Hold the syringe and press the plunger all the way down until the syringe is empty (see Figure H).
- Then take your thumb off the plunger to let the needle retract into the body of the syringe.

Step 8: Remove the syringe

- Pull the syringe away from your skin at the same angle that you pushed it in.
- Make sure that the needle has retracted (see Figure I).
- Not sure if you received your dose? Call 1-833-267-3070.

Step 9: How should I throw away (dispose of) the used prefilled syringes?

- Put your used syringes in an FDA-cleared sharps disposal container right away after use. Do not throw away (dispose of) syringes in your household trash (see Figure I).
- If you do not have an FDA-cleared sharps disposal container, you may use a household container that is:
  - made of a heavy-duty plastic,
  - can be closed with a tight-fitting, puncture-resistant lid, without sharps being able to come out,
  - upright and stable during use,
  - leak-resistant, and
  - properly labeled to warn of hazardous waste inside the container.
- When your sharps disposal container is almost full, you will need to follow your community guidelines for the right way to dispose of sharps disposal containers. There may be state or local laws about how you should throw away used syringes. For more information about safe sharps disposal, and for specific information about sharps disposal in the state that you live in, go to the FDA’s website at: http://www.fda.gov/safesharpsdisposal.
- Do not dispose of your used sharps disposal container in your household trash unless your community guidelines permit this. Do not recycle your used sharps disposal container.

Extra tips for injecting Adalimumab-bwwd

Now that you understand the basics of giving yourself an injection, here are some extra tips to help you.

Choose a fatty area for injection

- Fatty areas, like your stomach, are generally the best injection sites. Fatty areas are easier to pinch and are good for inserting the needle correctly.

Use a different injection site every time

- When choosing an injection site, select an area that has not recently been used to avoid soreness and bruises.

Finalize your injection

- After the injection is complete, you can use a cotton ball or gauze to cover the injection site if there is a little bleeding.

Frequently asked questions (FAQs)

If you have questions, read through these FAQs to learn more. If you still have any questions, call 1-833-267-3070.

What should I do if:

My syringe is out of the refrigerator for more than 30 minutes

- It is okay to leave your syringe out for up to 14 days before injecting, as long as it is kept away from sunlight and indoor light. If your syringe has been at room temperature for more than 14 days, call 1-833-267-3070.

The medicine in my syringe is not clear, colorless to pale brown, free of particles, or is expired

- If the medicine in your syringe is not clear, colorless to pale brown, or free of particles, do not use it. If it is expired, do not use it. Get a new syringe. Call 1-833-267-3070.

I see air bubbles in my syringe

- It is normal to see small air bubbles in your syringe. There is no reason to remove them.

I took off my needle cap before I was ready to inject

- Do not put the needle cap back on. This could bend or damage the needle. You might accidentally stick yourself or waste the medicine. Call 1-833-267-3070.

I dropped my syringe

- If you dropped your syringe with the cap on, it is okay to use the syringe.
  If you dropped your syringe with the cap off, do not use it. The needle might be dirty or damaged. Call 1-833-267-3070.

The syringe is damaged or broken

- Do not use a damaged syringe. Get a new syringe. Call 1-833-267-3070.

The needle never retracted

- If the needle never retracted into the body, the plunger was not pushed all the way down. Press the plunger harder to activate the shield. If you still have trouble, call 1-833-267-3070.

I am not sure I received my full dose

- You received your full dose if:
  - The plunger was pushed all the way down
  - The needle retracted into the shield
  - All of the medicine went into your skin and did not leak out. (If you see a drop, that is okay)
- If you are still not sure, call 1-833-267-3070.

This Instructions for Use has been approved by the U.S. Food and Drug Administration.

Manufactured by: Samsung Bioepis Co., Ltd., 76, Songdogyoyuk-ro, Yeonsu-gu, Incheon, 21987, Republic of Korea

U.S. License No. 2046

Manufactured for: Cordavis Limited, Dublin, Ireland

Last Revised <10/2025>

INSTRUCTIONS FOR USE

Adalimumab-bwwd (ada-LIM-u-mab bwwd)
40 mg/0.4 mL
Single Dose Autoinjector

For subcutaneous (under the skin) use only

Do not try to inject Adalimumab-bwwd yourself until you have been shown the right away to give an injection and have read and understand this Instructions for Use. If your doctor decides that you or a caregiver may be able to give your injections of Adalimumab-bwwd at home, you should receive training on the right way to prepare and inject Adalimumab-bwwd. It is important that you read, understand, and follow these instructions so that you inject Adalimumab-bwwd the right way. Call your healthcare provider if you or your caregiver have any questions about the right way to inject Adalimumab-bwwd.

To help you remember when to inject Adalimumab-bwwd, you can mark your calendar ahead of time.

The following instructions are for preparing and giving 1 dose of Adalimumab-bwwd autoinjector. Read this Instructions for Use before you start using Adalimumab-bwwd autoinjector.

What is included in this Instructions for Use

- Your Adalimumab-bwwd autoinjector
- Caring for your autoinjector
- How to inject with your autoinjector
- How should I throw away (dispose of) the used autoinjectors?
- Extra tips for injecting Adalimumab-bwwd
- Frequently asked questions (FAQs)

Your Adalimumab-bwwd autoinjector:

The needle is hidden below the green base. When you push the Adalimumab-bwwd autoinjector onto your skin, the injection will start automatically.

Important: There is no button on your Adalimumab-bwwd autoinjector.

Caring for your autoinjector

How should I store Adalimumab-bwwd autoinjector?

Store Adalimumab-bwwd in the refrigerator between 36°F to 46°F (2°C to 8°C).

- Do not freeze Adalimumab-bwwd. Do not use Adalimumab-bwwd if frozen, even if it has been thawed.
- Refrigerated Adalimumab-bwwd may be used until the expiration date printed on the Adalimumab-bwwd carton or autoinjector. Do not use Adalimumab-bwwd after the expiration date.
- If needed, for example when you are traveling, you may also store Adalimumab-bwwd at room temperature up to 77°F (25°C) for up to 14 days. Throw away Adalimumab-bwwd if it has been kept at room temperature and not been used within 14 days.

Store Adalimumab-bwwd in the original carton until you use it to protect it from sunlight and indoor light.

- Record the date you first remove Adalimumab-bwwd from the refrigerator in the spaces provided on the carton.
- Do not store Adalimumab-bwwd in extreme heat or cold.
- Do not drop or crush Adalimumab-bwwd. The prefilled syringe is glass.

Keep Adalimumab-bwwd, injection supplies, and all other medicines out of the reach of children.

Use each Adalimumab-bwwd autoinjector only 1 time. Do not reuse Adalimumab-bwwd autoinjector.

Throw away your used Adalimumab-bwwd autoinjector in a sharps container.

If you have any questions, call the hotline at 1-833-267-3070.

How to inject with your autoinjector

Step 1: Remove your Adalimumab-bwwd autoinjector from the refrigerator and wait 15 to 30 minutes

- For a more comfortable injection, you should wait 15 to 30 minutes for the medicine in autoinjector to reach room temperature (see Figure B).
- Do not warm Adalimumab-bwwd in any other way (for example, do not warm it in a microwave or in hot water).

Step 2: Gather supplies

- You will need the following supplies for each injection of Adalimumab-bwwd (see Figure C).
  Find a clean, flat surface to place the supplies on.
  - 1 Adalimumab-bwwd autoinjector
  - 1 alcohol swab (not included in your Adalimumab-bwwd carton)
  - cotton ball or gauze (not included in your Adalimumab-bwwd carton)
  - puncture-resistant sharps disposal container for Adalimumab-bwwd autoinjector disposal (not included in your Adalimumab-bwwd carton). See “How should I throw away (dispose of) the used autoinjectors?” section at the end of this Instructions for Use.

If you do not have all the supplies you need to give yourself an injection, go to a pharmacy or call your pharmacist.

Step 3: Inspect the medicine and check the expiration date

- You should always check the expiration date to make sure your autoinjector has not expired. Do not use if the expiration date has passed.
- Do not use Adalimumab-bwwd if:
  - the autoinjector is frozen or has been left in sunlight and indoor light.
  - it has been kept at room temperature for longer than 14 days or Adalimumab-bwwd has been stored above 77°F (25 °C).
  - see the “Caring for your autoinjector” and “Frequently asked questions (FAQs)” sections of this Instructions for Use.
- The solution should be clear and colorless to pale brown. Do not use the autoinjector if the liquid is cloudy, discolored, or has flakes or particles in it (see Figure D).
- You may see one or more air bubbles in the medicine window, and that is okay. There is no reason to remove it.
- Do not remove the needle cap until Step 5.

Step 4: Choose the injection site and clean the skin

- Wash and dry your hands.
- Choose an injection site on your body. The recommended injection site is the front of the thigh or lower abdomen (belly), but not the area 2 inches (5 cm) around your belly button (naval) (see Figure E).
- Choose a different site each time you give yourself an injection.
- Do not inject into areas where the skin is tender, bruised, red, scaly or hard. Avoid areas with scars or stretch marks. If you have psoriasis, you should not inject directly into areas with psoriasis plaques.
- Wipe your skin at the injection site with an alcohol swab in a circular motion. Let the skin dry before injecting.
- Do not touch this area again before giving the injection.

Step 5: Pull off the clear needle cap

- Carefully pull off the clear needle cap with a metal center straight off to remove it from the autoinjector (see Figure F).
- Throw away the needle cap.

Step 6: Place the green base of the autoinjector on your skin, press down, and hold

- Place the green base straight on your skin and push the entire device down firmly to start the injection.
- When you push down, the injection will start (see Figure G).
- You may hear the first click which means the injection has started.

Step 7: Keep holding the autoinjector

- Keep holding the autoinjector against your skin until the yellow indicator fills the medicine window and the yellow indicator stops moving (see Figure H).
- After a few seconds you may hear a second click. This means the injection is complete.

Step 8: Make sure the entire dose is given

- If the medicine window is all yellow, this means your dose is complete (see Figure I).
- Remove the autoinjector away from your skin. The needle should be covered by the green base.
- Not sure if you received your dose? Call 1-833-267-3070.

Step 9: How should I throw away (dispose of) the used autoinjectors?

- Put your used autoinjectors in an FDA-cleared sharps disposal container right away after use. Do not throw away (dispose of) autoinjectors in your household trash (see Figure I).
- If you do not have an FDA-cleared sharps disposal container, you may use a household container that is:
  - made of a heavy-duty plastic,
  - can be closed with a tight-fitting, puncture-resistant lid, without sharps being able to come out,
  - upright and stable during use,
  - leak-resistant, and
  - properly labeled to warn of hazardous waste inside the container.
- When your sharps disposal container is almost full, you will need to follow your community guidelines for the right way to dispose of sharps disposal containers. There may be state or local laws about how you should throw away used autoinjectors. For more information about safe sharps disposal, and for specific information about sharps disposal in the state that you live in, go to the FDA’s website at: http://www.fda.gov/safesharpsdisposal.
- Do not dispose of your used sharps disposal container in your household trash unless your community guidelines permit this. Do not recycle your used sharps disposal container.

Extra tips for injecting Adalimumab-bwwd

Now that you understand the basics of giving yourself an injection, here are some extra tips to help you.

Use a different injection site every time

- When choosing an injection site, select an area that has not recently been used to avoid soreness and bruises.

Finalize your injection

- After the injection is complete, you can use a cotton ball or gauze to cover the injection site if there is a little bleeding.

Frequently asked questions (FAQs)

If you have questions, read through these FAQs to learn more. If you still have any questions, call 1-833-267-3070.

What should I do if:

My autoinjector is out of the refrigerator for more than 30 minutes

- It is okay to leave your autoinjector out for up to 14 days before injecting, as long as it is kept away from sunlight and indoor light. If your Adalimumab-bwwd autoinjector has been at room temperature for more than 14 days, call 1-833-267-3070.

The medicine in my Adalimumab-bwwd autoinjector is not clear, colorless to pale brown, free of particles, or is expired

- If your medicine in your Adalimumab-bwwd autoinjector is not clear, colorless to pale brown, or free of particles, do not use it. If it is expired, do not use it. Get a new autoinjector. Call 1-833-267-3070.

I see air bubbles in my autoinjector

- It is normal to see small air bubbles in your autoinjector. There is no reason to remove them.

I took off my autoinjector cap before I was ready to inject

- Do not put the autoinjector cap back on. This could bend or damage the needle. You might accidentally stick yourself or waste the medicine. Call 1-833-267-3070.

I dropped my autoinjector

- If you dropped your autoinjector with the cap on, it is okay to use the autoinjector.
  If you dropped your autoinjector with the cap off, do not use it. The needle might be dirty or damaged. Call 1-833-267-3070.

The autoinjector is damaged or broken

- Do not use a damaged autoinjector. Get a new autoinjector. Call 1-833-267-3070.

The entire medicine window is not yellow after injection

- If your medicine window is not entirely yellow after injection, you may not have received your full dose. Call 1-833-267-3070.

I am not sure I received my full dose

- You received your full dose if:
  - The entire medicine window is yellow at the end of injection
  - All of the medicine went into your skin and did not leak out. (If you see a drop, that is okay)
- If you are still not sure, call 1-833-267-3070.

This Instructions for Use has been approved by the U.S. Food and Drug Administration.

Manufactured by: Samsung Bioepis Co., Ltd., 76, Songdogyoyuk-ro, Yeonsu-gu, Incheon, 21987, Republic of Korea

U.S. License No. 2046

Manufactured for: Cordavis Limited, Dublin, Ireland

Last Revised <10/2025>

PRINCIPAL DISPLAY PANEL - Single-dose Prefilled Syringe Carton - 40 mg/0.4 mL

Single-dose Prefilled Syringe Carton - 40 mg/0.4 mL

NDC 83457-186-01 40 mg/0.4 mL

Adalimumab-bwwd
injection
40 mg/0.4 mL
Single-Dose Prefilled Syringe

For Subcutaneous Use only

Dispense the enclosed
Medication Guide to each
patient.

2 single-dose prefilled syringes

The entire carton is
to be dispensed as a unit.

This carton contains:

- 2 single-dose prefilled syringes
- 1 package insert
  (Includes Medication Guide)
- 1 Instructions for Use

Rx only cordavis™

Manufactured for:
Cordavis Limited
Dublin, Ireland

Manufactured by:
Samsung Bioepis Co., Ltd.
Incheon, Republic of Korea

US License No. 2046
Product of Korea

Our hotline:
1-833-267-3070

PRINCIPAL DISPLAY PANEL - Single-dose Autoinjector Carton - 40 mg/0.4 mL

Single-dose Autoinjector Carton - 40 mg/0.4 mL

NDC 83457-187-01 40 mg/0.4 mL

Adalimumab-bwwd
injection
40 mg/0.4 mL
Single-Dose Prefilled Autoinjector

For Subcutaneous Use only

Dispense the enclosed
Medication Guide to each
patient.

2 single-dose prefilled
autoinjectors

The entire carton is
to be dispensed as a unit.

This carton contains:

- 2 single-dose prefilled
  autoinjectors
- 1 package insert
  (Includes Medication Guide)
- 1 Instructions for Use

There is NO BUTTON on your
autoinjector.

Rx only cordavis™

Manufactured for:
Cordavis Limited
Dublin, Ireland

Manufactured by:
Samsung Bioepis Co., Ltd.
Incheon, Republic of Korea

US License No. 2046
Product of Korea

Our hotline:
1-833-267-3070